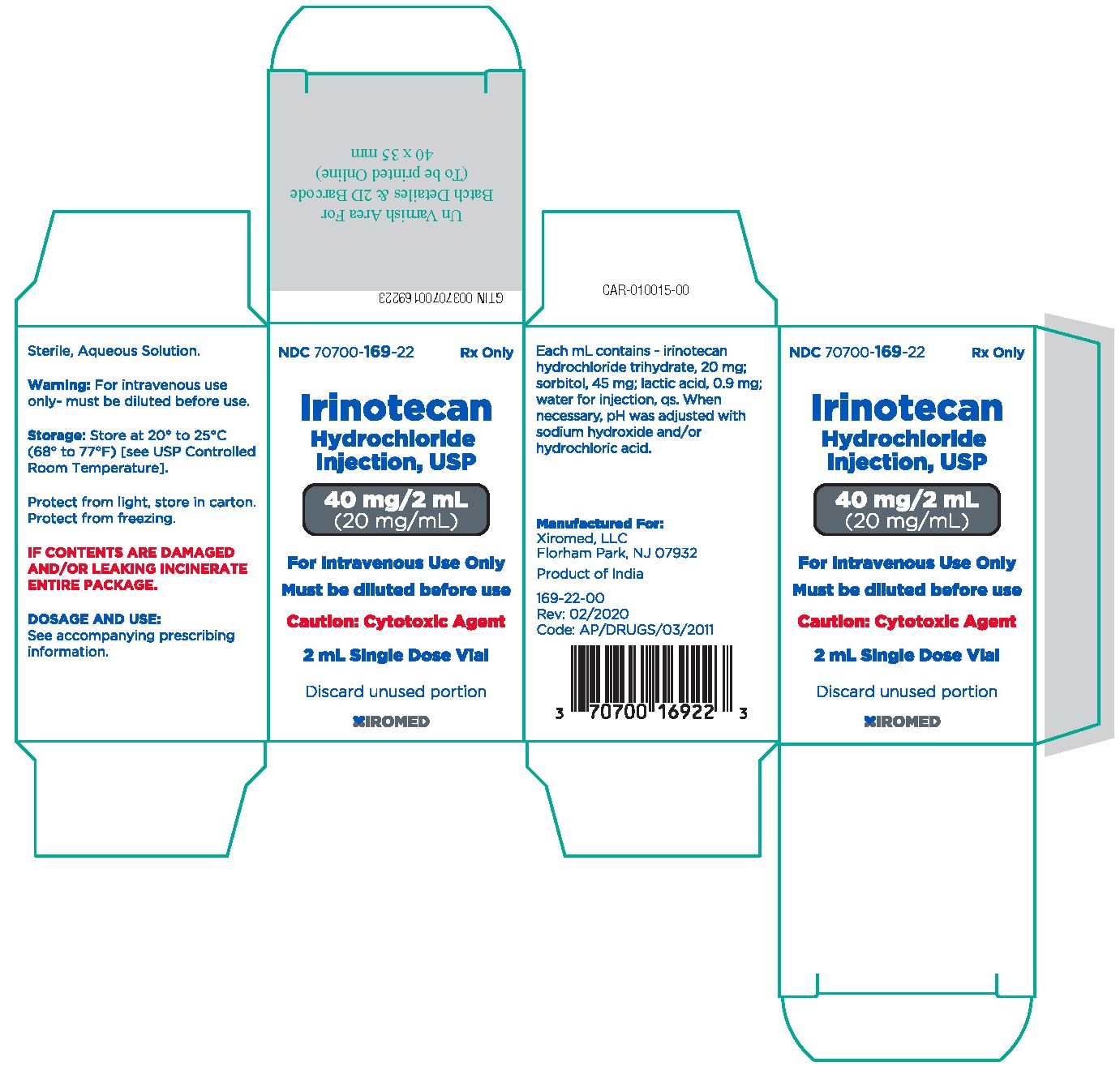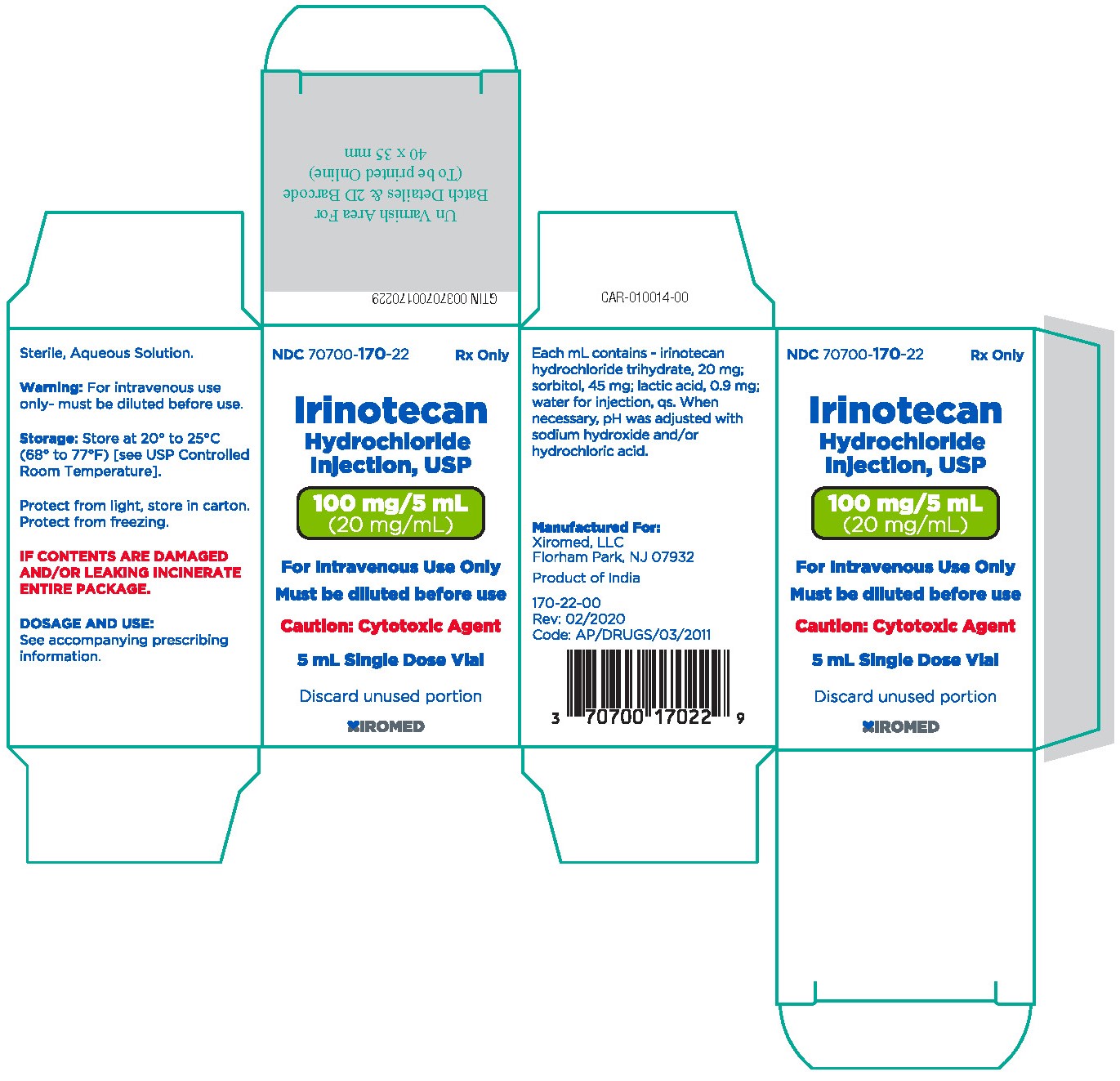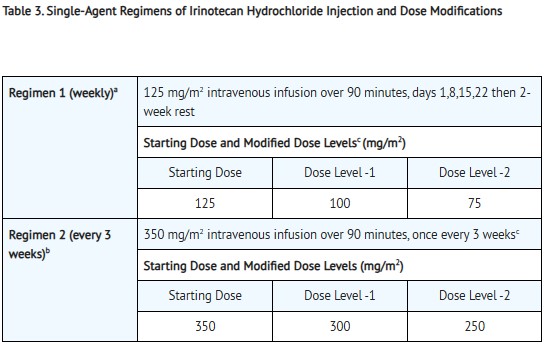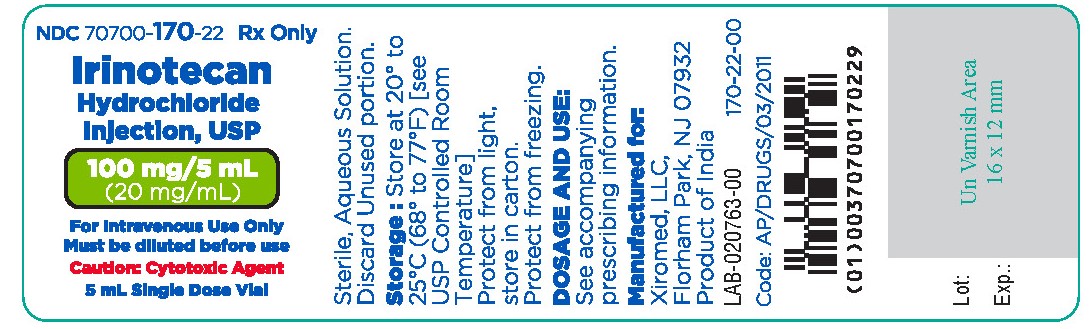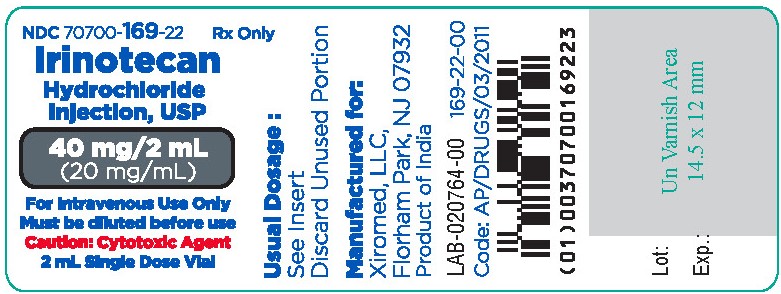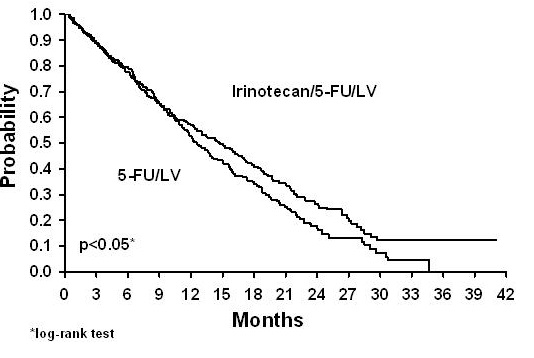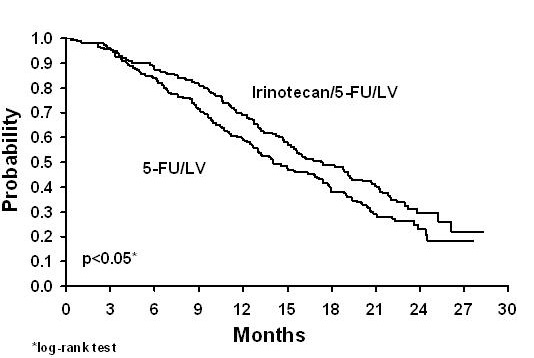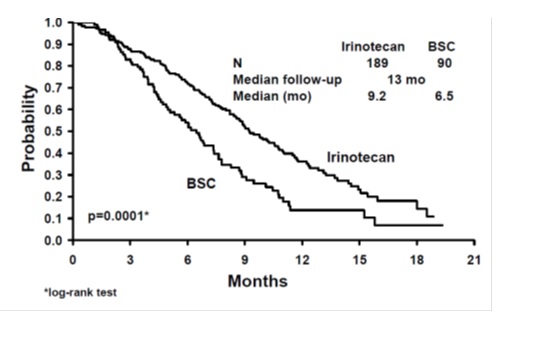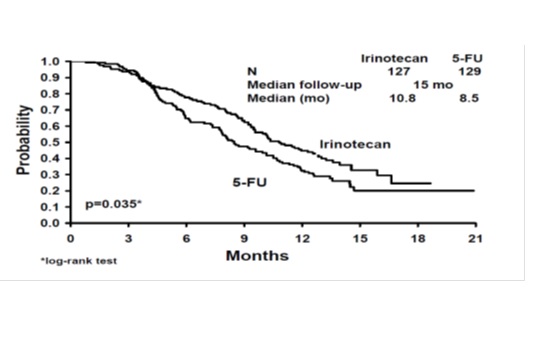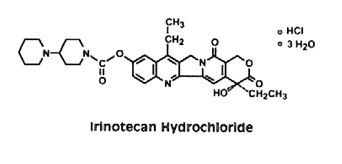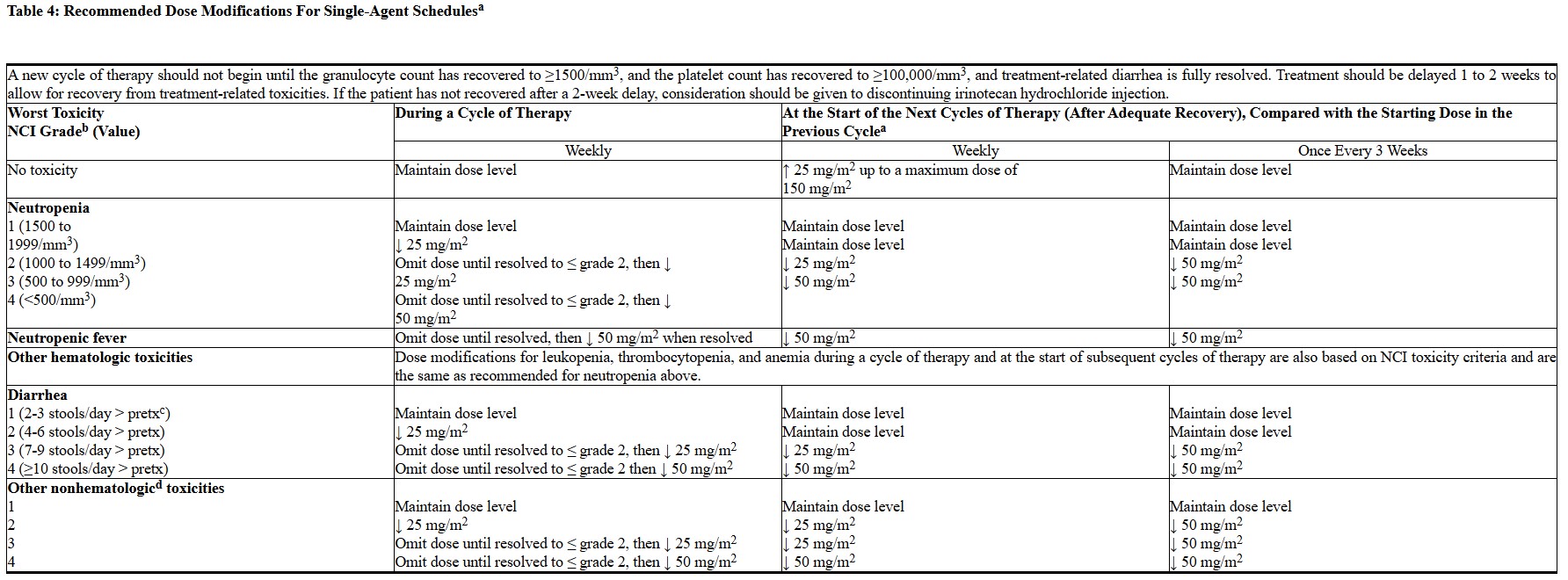 DRUG LABEL: Irinotecan hydrochloide
NDC: 70700-169 | Form: INJECTION
Manufacturer: Xiromed LLC
Category: prescription | Type: HUMAN PRESCRIPTION DRUG LABEL
Date: 20260219

ACTIVE INGREDIENTS: IRINOTECAN HYDROCHLORIDE 20 mg/1 mL
INACTIVE INGREDIENTS: LACTIC ACID; SODIUM HYDROXIDE; HYDROCHLORIC ACID; SORBITOL

HIGHLIGHTS OF PRESCRIBING INFORMATION

These highlights do not include all the information needed to use IRINOTECAN HYDROCHLORIDE INJECTION safely and effectively. See full prescribing information for IRINOTECAN HYDROCHLORIDE INJECTION.
IRINOTECAN HYDROCHLORIDE injection, for intravenous use
Initial U.S. Approval: 1996

RECENT MAJOR CHANGES

Dosage and Administration, Dosage in Patients With Reduced UGT1A1 Activity (2.3) 1/2022

Dosage and Administration, Preparation of Infusion Solution (2.5) 1/2022

Dosage and Administration, Safe Handling (2.6) 1/2022

Warnings and Precautions, Increased Risk of Neutropenia in Patients With Reduced UGT1A1 Activity (5.3) 1/2022

WARNING: DIARRHEA and MYELOSUPPRESSION

See full prescribing information for complete boxed warning.

- Early and late forms of diarrhea can occur. Early diarrhea may be accompanied by cholinergic symptoms which may be prevented or ameliorated by atropine. Late diarrhea can be life threatening and should be treated promptly with loperamide. Monitor patients with diarrhea and give fluid and electrolytes as needed. Institute antibiotic therapy if patients develop ileus, fever, or severe neutropenia. Interrupt irinotecan hydrochloride injection and reduce subsequent doses if severe diarrhea occurs [see Dosage and Administration (2.2)and Warnings and Precautions (5.1)].
- Severe myelosuppression may occur [see Warnings and Precautions (5.2)].

1 INDICATIONS AND USAGE

Irinotecan hydrochloride injection is a topoisomerase inhibitor indicated for:

- First-line therapy in combination with 5-fluorouracil and leucovorin for patients with metastatic carcinoma of the colon or rectum. (1)
- Patients with metastatic carcinoma of the colon or rectum whose disease has recurred or progressed following initial fluorouracil-based therapy. (1)

2 DOSAGE AND ADMINISTRATION

- Colorectal cancer combination regimen 1: Irinotecan hydrochloride injection 125 mg/m^2intravenous infusion over 90 minutes on days 1, 8, 15, 22 with LV 20 mg/m^2intravenous bolus infusion on days 1, 8, 15, 22 followed by 5-FU intravenous bolus infusion on days 1, 8, 15, 22 every 6 weeks. (2.1)
- Colorectal cancer combination regimen 2: Irinotecan hydrochloride injection 180 mg/m^2intravenous infusion over 90 minutes on days 1, 15, 29 with LV 200 mg/m^2intravenous infusion over 2 hours on days 1, 2, 15, 16, 29, 30 followed by 5-FU 400 mg/m^2intravenous bolus infusion on days 1, 2, 15, 16, 29, 30 and 5-FU 600 mg/m^2intavenous infusion over 22 hours on days 1, 2, 15, 16, 29, 30. (2.1)
- Colorectal cancer single agent regimen 1: Irinotecan hydrochloride injection 125 mg/ m^2intravenous infusion over 90 minutes on days 1, 8, 15, 22 then 2-week rest. (2.2)
- Colorectal cancer single agent regimen 2: Irinotecan hydrochloride injection 350 mg/ m^2intravenous infusion over 90 minutes on day 1 every 3 weeks. (2.2)

3 DOSAGE FORMS AND STRENGTHS

Injection: 40 mg/2 mL (20 mg/mL) and 100 mg/5 mL (20 mg/mL) solution in a single-dose vial. (3)

4 CONTRAINDICATIONS

• Hypersensitivity to irinotecan hydrochloride injection or its excipients (4)

5 WARNINGS AND PRECAUTIONS

• Diarrhea and Cholinergic Reactions:Early diarrhea (occurring during or shortly after infusion of irinotecan hydrochloride injection) is usually transient and may be accompanied by cholinergic symptoms. Consider prophylactic or therapeutic administration of 0.25 mg to 1 mg of intravenous or subcutaneous atropine (unless clinically contraindicated). Late diarrhea (generally occurring more than 24 hours after administration of irinotecan hydrochloride injection) can occur. Monitor and replace fluid and electrolytes. Treat with loperamide. Use antibiotic support for ileus and fever. Interrupt irinotecan hydrochloride injection and reduce subsequent doses if severe diarrhea occurs. (5.1)
• Myelosuppression:Manage promptly with antibiotic support. Interrupt irinotecan hydrochloride injection and reduce subsequent doses if necessary. (5.2)
• Increased Risk of Neutropenia in Patients with Reduced UGT1A1 Activity:Individuals with UGT1A1 *28/*28, or *6/*6, or *6/*28 genotypes are at increased risk for severe neutropenia during irinotecan hydrochloride injection treatment. (5.3)
• Hypersensitivity:Hypersensitivity reactions including severe anaphylactic or anaphylactoid reactions have been observed. Discontinue irinotecan hydrochloride injection if this occurs. (5.4)
• Renal Impairment/Renal Failure:Rare cases of renal impairment and acute renal failure have been identified, usually in patients who became volume depleted from severe vomiting and/or diarrhea. (5.5)
• Pulmonary Toxicity: Interstitial Pulmonary Disease (IPD)-like events, including fatalities, have occurred. Interrupt for new or progressive dyspnea, cough, and fever pending evaluation. If IPD diagnosed, discontinue and institute appropriate treatment as needed. (5.6)
• Toxicity of the 5 Day Regimen:Irinotecan hydrochloride injection should not be used in combination with a regimen of 5-FU/LV administered for 4-5 consecutive days every 4 weeks outside of a clinical study. (5.7)
• Embryo-Fetal Toxicity:Irinotecan hydrochloride injection can cause fetal harm. Advise females of reproductive potential of the potential risk to a fetus and to use effective contraception. Advise male patients with female partners of reproductive potential to use condoms. (5.9, 8.1, 8.3)
• Patients With Hepatic Impairment:In clinical trials, irinotecan hydrochloride injection has not been administered to patients with serum bilirubin > 2.0 mg/dL, or transaminases > 3 times ULN if no liver metastases, or transaminases > 5 times ULN if liver metastases. With the weekly dosage schedule, patients with total bilirubin levels 1.0-2.0 mg/dL had greater likelihood of grade 3-4 neutropenia. (5.10)

6 ADVERSE REACTIONS

Common adverse reactions (≥30%) observed in single agent therapy clinical studies are: nausea, vomiting, abdominal pain, diarrhea, constipation, anorexia, mucositis, neutropenia, leukopenia (including lymphocytopenia), anemia, thrombocytopenia, asthenia, pain, fever, infection, abnormal bilirubin, alopecia. (6.1)

Common adverse reactions (≥30%) observed in single agent therapy clinical studies are: nausea, vomiting, abdominal pain, diarrhea, constipation, anorexia, neutropenia, leukopenia (including lymphocytopenia), anemia, asthenia, fever, body weight decreasing, alopecia. (6.1)

To report SUSPECTED ADVERSE REACTIONS, contact Xiromed LLC at 844-XIROMED (1-844-947-6633) or FDA at 1-800-FDA-1088 or www.fda.gov/medwatch.

7 DRUG INTERACTIONS

• Strong CYP3A4 Inducers:Do not administer strong CYP3A4 inducers with irinotecan hydrochloride injection. (7.2)
• Strong CYP3A4 Inhibitors:Do not administer strong CYP3A4 inhibitors with irinotecan hydrochloride injection. (7.3)

8 USE IN SPECIFIC POPULATIONS

• Lactation:Advise not to breastfeed. (8.2)
• Geriatric Use:Closely monitor patients greater than 65 years of age because of a greater risk of early and late diarrhea in this population. (8.5)
• Patients With Renal Impairment:Use caution and do not use in patients on dialysis. (8.6)
• Patients With Hepatic Impairment:Use caution. (2.1, 5.10, 8.7, 12.3)

FULL PRESCRIBING INFORMATION

WARNING: DIARRHEA and MYELOSUPPRESSION

• Early and late forms of diarrhea can occur. Early diarrhea may be accompanied by cholinergic symptoms which may be prevented or ameliorated by atropine. Late diarrhea can be life threatening and should be treated promptly with loperamide. Monitor patients with diarrhea and give fluid and electrolytes as needed. Institute antibiotic therapy if patients develop ileus, fever, or severe neutropenia. Interrupt irinotecan hydrochloride injection and reduce subsequent doses if severe diarrhea occurs. (2.2, 5.1)

• Severe myelosuppression may occur. (5.2)

1 INDICATIONS AND USAGE

- Irinotecan hydrochloride injection is indicated as a component of first-line therapy in combination with 5-fluorouracil (5-FU) and leucovorin (LV) for patients with metastatic carcinoma of the colon or rectum.
- Irinotecan hydrochloride injection is indicated for patients with metastatic carcinoma of the colon or rectum whose disease has recurred or progressed following initial fluorouracil-based therapy.

2 DOSAGE AND ADMINISTRATION

2.1 Colorectal Cancer Combination Regimens 1 and 2

Administer irinotecan hydrochloride injection as a 90-minute intravenous infusion followed by LV and 5-FU. The currently recommended regimens are shown in Table 1.

A reduction in the starting dose by one dose level of irinotecan hydrochloride injection may be considered for patients with any of the following conditions: prior pelvic/abdominal radiotherapy, performance status of 2, or increased bilirubin levels. Dosing for patients with bilirubin >2 mg/dL cannot be recommended because there is insufficient information to recommend a dose in these patients.

Table 1: Combination-Agent Dosage Regimens and Dose Modificationsa

Regimen 1 6-wk cycle with bolus 5-FU/LV (next cycle begins on day 43) | Irinotecan Hydrochloride Injection LV 5-FU | 125 mg/m^2intravenous infusion over 90 minutes, days 1,8,15,22 20 mg/m^2intravenous injection bolus, days 1,8,15,22 500 mg/m^2intravenous injection bolus, days 1,8,15,22
Regimen 1 6-wk cycle with bolus 5-FU/LV (next cycle begins on day 43) | Irinotecan Hydrochloride Injection LV 5-FU | Starting Dose & Modified Dose Levels (mg/m^2)
Regimen 1 6-wk cycle with bolus 5-FU/LV (next cycle begins on day 43) | Irinotecan Hydrochloride Injection LV 5-FU | Starting Dose | Dose Level -1 | Dose Level -2
Regimen 1 6-wk cycle with bolus 5-FU/LV (next cycle begins on day 43) | Irinotecan Hydrochloride Injection LV 5-FU | 125 20 500 | 100 20 400 | 75 20 300

Regimen 2 6-wk cycle with infusional 5-FU/LV (next cycle begins on day 43) | Irinotecan Hydrochloride Injection LV 5-FU Bolus 5-FU Infusionb | 180 mg/m^2intravenous infusion over 90 minutes, days 1,15,29 200 mg/m^2intravenous infusion over 2 hours, days 1,2,15,16,29,30 400 mg/m^2intravenous injection bolus, days 1,2,15,16,29,30 600 mg/m^2intravenous infusion over 22 hours, days 1,2,15,16,29,30
Regimen 2 6-wk cycle with infusional 5-FU/LV (next cycle begins on day 43) | Irinotecan Hydrochloride Injection LV 5-FU Bolus 5-FU Infusionb | Starting Dose & Modified Dose Levels (mg/m^2)
Regimen 2 6-wk cycle with infusional 5-FU/LV (next cycle begins on day 43) | Irinotecan Hydrochloride Injection LV 5-FU Bolus 5-FU Infusionb | Starting Dose | Dose Level -1 | Dose Level -2
Regimen 2 6-wk cycle with infusional 5-FU/LV (next cycle begins on day 43) | Irinotecan Hydrochloride Injection LV 5-FU Bolus 5-FU Infusionb | 180 200 400 600 | 150 200 320 480 | 120 200 240 360

aDose reductions beyond Dose Level –2 by decrements of ≈ 20% may be warranted for patients continuing to experience toxicity. Provided intolerable toxicity does not develop, treatment with additional cycles may be continued indefinitely as long as patients continue to experience clinical benefit.

bInfusion follows bolus administration.

Dosing for patients with bilirubin >2 mg/dL cannot be recommended because there is insufficient information to recommend a dose in these patients [see Warnings and Precautions (5.10), Use in Specific Populations (8.7) and Clinical Pharmacology (12.3)] .

Dose Modifications

Based on recommended dose levels described in Table 1, Combination Regimens of irinotecan hydrochloride injection and Dose Modifications, subsequent doses should be adjusted as suggested in Table 2, Recommended Dose Modifications for Combination Regimens. All dose modifications should be based on the worst preceding toxicity.

Table 2: Recommended Dose Modifications for Irinotecan Hydrochloride Injection/5-Fluorouracil (5-FU)/Leucovorin (LV) Combination Schedules

Patients should return to pre-treatment bowel function without requiring antidiarrhea medications for at least 24 hours before the next chemotherapy administration. A new cycle of therapy should not begin until the granulocyte count has recovered to ≥1500/mm^3, and the platelet count has recovered to ≥100,000/mm^3, and treatment-related diarrhea is fully resolved. Treatment should be delayed 1 to 2 weeks to allow for recovery from treatment-related toxicities. If the patient has not recovered after a 2-week delay, consideration should be given to discontinuing therapy.
Toxicity NCI CTC Gradea(Value) | During a Cycle of Therapy | At the Start of Subsequent Cycles of Therapyb
No toxicity | Maintain dose level | Maintain dose level
Neutropenia 1 (1500 to 1999/mm^3) 2 (1000 to 1499/mm^3) 3 (500 to 999/mm^3) 4 (<500/mm^3) | Maintain dose level ↓ 1 dose level Omit dose until resolved to ≤ grade 2, then ↓ 1 dose level Omit dose until resolved to ≤ grade 2, then ↓ 2 dose levels | Maintain dose level Maintain dose level ↓ 1 dose level ↓ 2 dose levels
Neutropenic fever | Omit dose until resolved, then ↓ 2 dose levels
Other hematologic toxicities | Dose modifications for leukopenia or thrombocytopenia during a cycle of therapy and at the start of subsequent cycles of therapy are also based on NCI toxicity criteria and are the same as recommended for neutropenia above.
Diarrhea 1 (2 to 3 stools/day > pretxc) 2 (4 to 6 stools/day > pretx) 3 (7 to 9 stools/day > pretx) 4 (≥10 stools/day > pretx) | Delay dose until resolved to baseline, then give same dose Omit dose until resolved to baseline, then ↓ 1 dose level Omit dose until resolved to baseline, then ↓ 1 dose level Omit dose until resolved to baseline, then ↓ 2 dose levels | Maintain dose level Maintain dose level ↓ 1 dose level ↓ 2 dose levels
Other nonhematologic toxicitiesd 1 2 3 4 | Maintain dose level Omit dose until resolved to ≤ grade 1, then ↓ 1 dose level Omit dose until resolved to ≤ grade 2, then ↓ 1 dose level Omit dose until resolved to ≤ grade 2, then ↓ 2 dose levels For mucositis/stomatitis decrease only5-FU, not irinotecan hydrochloride injection | Maintain dose level Maintain dose level ↓ 1 dose level ↓ 2 dose levels For mucositis/stomatitis decrease only 5-FU, not irinotecan hydrochloride injection.

aNational Cancer Institute Common Toxicity Criteria (version 1.0)

bRelative to the starting dose used in the previous cycle

cPretreatment

dExcludes alopecia, anorexia, asthenia

2.2 Colorectal Single Agent Regimens 1 and 2

Administer irinotecan hydrochloride injection as a 90-minute intravenous infusion. The currently recommended regimens are shown in Table 3.

A reduction in the starting dose by one dose level of irinotecan hydrochloride injection may be considered for patients with any of the following conditions: prior pelvic/abdominal radiotherapy, performance status of 2, or increased bilirubin levels. Dosing for patients with bilirubin >2 mg/dL cannot be recommended because there is insufficient information to recommend a dose in these patients.

aSubsequent doses may be adjusted as high as 150 mg/m^2or to as low as 50 mg/m^2in 25 to 50 mg/m^2decrements depending upon individual patient tolerance.
bSubsequent doses may be adjusted as low as 200 mg/m^2in 50 mg/m^2decrements depending upon individual patient tolerance.
cProvided intolerable toxicity does not develop, treatment with additional cycles may be continued indefinitely as long as patients continue to experience clinical benefit.
Dose Modifications
Based on recommended dose-levels described in Table 3, Single-Agent Regimens of irinotecan hydrochloride injection and Dose Modifications, subsequent doses should be adjusted as suggested in Table 4, Recommended Dose Modifications for Single-Agent Schedules. All dose modifications should be based on the worst preceding toxicity.

aAll dose modifications should be based on the worst preceding toxicity
bNational Cancer Institute Common Toxicity Criteria (version 1.0)
cPretreatment
dExcludes alopecia, anorexia, asthenia

2.3 Dosage in Patients With Reduced UGT1A1 Activity

When administered in combination with other agents, or as a single-agent, consider a reduction in the starting dose by at least one level of irinotecan hydrochloride injection for patients known to be homozygous for the UGT1A1*28 or *6 alleles (*28/*28, *6/*6) or compound heterozygous for the UGT1A1*28 and *6 alleles (*6/*28) [see Dosage and Administration(2.1, 2.2), Warnings and Precautions (5.3), and Clinical Pharmacology (12.3, 12.5)]. Subsequent dosage modifications may be required based on individual patient tolerance to treatment [see Dosage and Administration (2.1, 2.2)].

2.4 Premedication

It is recommended that patients receive premedication with antiemetic agents. In clinical studies of the weekly dosage schedule, the majority of patients received 10 mg of dexamethasone given in conjunction with another type of antiemetic agent, such as a 5-HT^3blocker (e.g., ondansetron or granisetron). Antiemetic agents should be given on the day of treatment, starting at least 30 minutes before administration of irinotecan hydrochloride injection. Physicians should also consider providing patients with an antiemetic regimen (e.g., prochlorperazine) for subsequent use as needed. A similar antiemitic regiment should be used with irinotecan hydrochloride injection in combination therapy.

Prophylactic or therapeutic administration of atropine should be considered in patients experiencing cholinergic symptoms.

2.5 Preparation of Infusion Solution

Inspect vial contents for particulate matter and discoloration and repeat inspection when drug product is withdrawn from vial into syringe.

Irinotecan hydrochloride injection 20 mg/mL is intended for single use only and any unused portion should be discarded.

Irinotecan hydrochloride injection must be diluted prior to infusion using aseptic technique. Irinotecan hydrochloride injection should be diluted in 5% Dextrose Injection, USP, (preferred) or 0.9% Sodium Chloride Injection, USP, to a final concentration range of 0.12 mg/mL to 2.8 mg/mL. Other drugs should not be added to the infusion solution.

Prepare the infusion solution immediately prior to use and commence infusion as soon as possible after preparation. If visible particulates are present in the infusion solution discard. If it is not possible to use the infusion solution immediately, the infusion solution may be stored for up to 24 hours at 2 °C to 8 °C or discarded.

2.6 Safe Handling

Irinotecan hydrochloride injection is a hazardous drug. Follow applicable special handling and disposal procedures.^1

Care should be exercised in the handling and preparation of infusion solutions prepared from irinotecan hydrochloride injection. The use of gloves is recommended. If a solution of irinotecan hydrochloride injection contacts the skin, wash the skin immediately and thoroughly with soap and water. If irinotecan hydrochloride injection contacts the mucous membranes, flush thoroughly with water.

2.7 Extravasation

Care should be taken to avoid extravasation, and the infusion site should be monitored for signs of inflammation. Should extravasation occur, flushing the site with sterile water and applications of ice are recommended.

3 DOSAGE FORMS AND STRENGTHS

Injection: 40 mg/2 mL (20 mg/mL) and 100 mg/5 mL (20 mg/mL) solution in a single-dose vial.

4 CONTRAINDICATIONS

• Irinotecan hydrochloride injection is contraindicated in patients with a known hypersensitivity to the drug or its excipients.

5 WARNINGS AND PRECAUTIONS

5.1 Diarrhea and Cholinergic Reactions

Early diarrhea (occurring during or shortly after infusion of irinotecan hydrochloride injection) is usually transient and infrequently severe. It may be accompanied by cholinergic symptoms of rhinitis, increased salivation, miosis, lacrimation, diaphoresis, flushing, and intestinal hyperperistalsis that can cause abdominal cramping. Bradycardia may also occur. Early diarrhea and other cholinergic symptoms may be prevented or treated. Consider prophylactic or therapeutic administration of 0.25 mg to 1 mg of intravenous or subcutaneous atropine (unless clinically contraindicated). These symptoms are expected to occur more frequently with higher irinotecan doses.

Late diarrhea (generally occurring more than 24 hours after administration of irinotecan hydrochloride injection) can be life threatening since it may be prolonged and may lead to dehydration, electrolyte imbalance, or sepsis. Grade 3 to 4 late diarrhea occurred in 23 to 31% of patients receiving weekly dosing. In the clinical studies, the median time to the onset of late diarrhea was 5 days with 3-week dosing and 11 days with weekly dosing. Late diarrhea can be complicated by colitis, ulceration, bleeding, ileus, obstruction, and infection. Cases of megacolon and intestinal perforation have been reported. Patients should have loperamide readily available to begin treatment for late diarrhea. Begin loperamide at the first episode of poorly formed or loose stools or the earliest onset of bowel movements more frequent than normal. One dosage regimen for loperamide is 4 mg at the first onset of late diarrhea and then 2 mg every 2 hours until the patient is diarrhea-free for at least 12 hours. Loperamide is not recommended to be used for more than 48 consecutive hours at these doses, because of the risk of paralytic ileus. During the night, the patient may take 4 mg of loperamide every 4 hours. Monitor and replace fluid and electrolytes. Use antibiotic support for ileus, fever, or severe neutropenia. Subsequent weekly chemotherapy treatments should be delayed in patients until return of pretreatment bowel function for at least 24 hours without anti-diarrhea medication. Patients must not be treated with irinotecan hydrochloride injection until resolution of the bowel obstruction. If grade 2, 3, or 4 late diarrhea recurs, subsequent doses of irinotecan hydrochloride injection should be decreased [see Dosage and Administration (2)].

Avoid diuretics or laxatives in patients with diarrhea.

5.2 Myelosuppression

Irinotecan hydrochloride injection can cause severe myelosuppression. Bacterial, viral and fungal infections have occurred in patients treated with irinotecan hydrochloride injection.
Deaths due to sepsis following severe neutropenia have been reported in patients treated with irinotecan hydrochloride injection. In the clinical studies evaluating the weekly dosage schedule, neutropenic fever (concurrent NCI grade 4 neutropenia and fever of grade 2 or greater) occurred in 3% of the patients; 6% of patients received G-CSF for the treatment of neutropenia. Manage febrile neutropenia promptly with antibiotic support [see Warnings and Precautions (5.2)]. Hold irinotecan hydrochloride injection if neutropenic fever occurs or if the absolute neutrophil count drops <1000/mm^3. After recovery to an absolute neutrophil count ≥1000/mm^3, subsequent doses of irinotecan hydrochloride injection should be reduced [see Dosage and Administration (2)].

When evaluated in the trials of weekly administration, the frequency of grade 3 and 4 neutropenia was higher in patients who received previous pelvic/abdominal irradiation than in those who had not received such irradiation (48% [13/27] versus 24% [67/277]; p=0.04). Patients who have previously received pelvic/abdominal irradiation are at increased risk of severe myelosuppression following the administration of irinotecan hydrochloride injection. Based on sparse available data, the concurrent administration of irinotecan hydrochloride injection with irradiation is not recommended.

Patients with baseline serum total bilirubin levels of 1.0 mg/dL or more also had a greater likelihood of experiencing first-cycle grade 3 or 4 neutropenia than those with bilirubin levels that were less than 1.0 mg/dL (50% [19/38] versus 18% [47/266]; p<0.001). Patients with deficient glucuronidation of bilirubin, such as those with Gilbert’s syndrome, may be at greater risk of myelosuppression when receiving therapy with irinotecan hydrochloride injection [see Warnings and Precautions (5.3)] .

5.3 Increased Risk of Neutropenia in Patients With Reduced UGT1A1 Activity

Published studies have shown that individuals who are homozygous for either the UGT1A1*28 or *6 alleles (*28/*28, *6/*6) or who are compound or double heterozygous for the UGT1A1*28 and *6 alleles (*6/*28) are at increased risk for severe or life-threatening neutropenia during treatment with irinotecan hydrochloride injection. These individuals are UGT1A1 poor metabolizers and experience increased systemic exposure to SN-38, an active metabolite of irinotecan. Individuals who are heterozygous for either the UGT1A1*28 or *6 alleles (*1/*28, *1/*6) are intermediate metabolizers and may also have an increased risk of severe or life-threatening neutropenia [see Dosage and Administration (2) and Clinical Pharmacology (12.3, 12.5) ].

Consider UGT1A1 genotype testing for the *28 and *6 alleles to determine UGT1A1 metabolizer status [see Clinical Pharmacology (12.5) ].

When administering irinotecan hydrochloride injection, consider a reduction in the irinotecan hydrochloride injection starting dose by at least one level for patients known to be homozygous or compound heterozygous for the UGT1A1*28 and/or *6 alleles (*28/*28, *6/*6, *6/*28).

Closely monitor patients with UGT1A1*28 or *6 alleles for neutropenia during and after treatment with irinotecan hydrochloride injection. The precise dosage reduction in this patient population is not known. Subsequent dosage modifications may be required based on individual patient tolerance to treatment [see Dosage and Administration (2.1, 2.2) ].

5.4 Hypersensitivity

Hypersensitivity reactions including severe anaphylactic or anaphylactoid reactions have been observed. Discontinue irinotecan hydrochloride injection if anaphylactic reaction occurs.

5.5 Renal Impairment/Renal Failure

Renal impairment and acute renal failure have been identified, usually in patients who became volume depleted from severe vomiting and/or diarrhea.

5.6 Pulmonary Toxicity

Interstitial Pulmonary Disease (IPD)-like events, including fatalities, have occurred in patients receiving irinotecan (in combination and as monotherapy). Risk factors include pre-existing lung disease, use of pneumotoxic drugs, radiation therapy, and colony stimulating factors. Patients with risk factors should be closely monitored for respiratory symptoms before and during irinotecan hydrochloride injection therapy. In Japanese studies, a reticulonodular pattern on chest x-ray was observed in a small percentage of patients. New or progressive, dyspnea, cough, and fever should prompt interruption of chemotherapy, pending diagnostic evaluation. If IPD is diagnosed, irinotecan hydrochloride injection and other chemotherapy should be discontinued and appropriate treatment instituted as needed [see Adverse Reactions (6.1)].

5.7 Toxicity of the 5 Day Regimen

Outside of a well-designed clinical study, irinotecan hydrochloride injection should not be used in combination with a regimen of 5-FU/LV administered for 4 to 5 consecutive days every 4 weeks because of reports of increased toxicity, including toxic deaths. Irinotecan hydrochloride injection should be used as recommended in Table 2 [see Dosage and Administration (2)].

5.8 Increased Toxicity in Patients With Performance Status 2

In patients receiving either irinotecan/5-FU/LV or 5-FU/LV in the clinical trials, higher rates of hospitalization, neutropenic fever, thromboembolism, first-cycle treatment discontinuation, and early deaths were observed in patients with a baseline performance status of 2 than in patients with a baseline performance status of 0 or 1.

5.9 Embryo-Fetal Toxicity

Based on its mechanism of action and findings in animals, irinotecan hydrochloride injection can cause fetal harm when administered to pregnant women. In animal studies, intravenous administration of irinotecan during the period of organogenesis resulted in embryofetal mortality and teratogenicity in pregnant animals at exposures lower than the human exposure based on area under the curve (AUC) at the clinical dose of 125 mg/m^2. Advise pregnant women of the potential risk to a fetus.
Advise female patients of reproductive potential to avoid becoming pregnant and to use highly effective contraception during treatment with irinotecan hydrochloride injection and for 6 months after the final dose. Advise male patients with female partners of reproductive potential to use condoms during treatment and for 3 months after the final dose of irinotecan hydrochloride injection [see Use in Specific Populations (8.1), (8.3) and Nonclinical Toxicology (13.1)].

5.10 Patients With Hepatic Impairment

The use of irinotecan hydrochloride injection in patients with significant hepatic impairment has not been established. In clinical trials of either dosing schedule, irinotecan was not administered to patients with serum bilirubin >2.0 mg/dL, or transaminase >3 times the upper limit of normal if no liver metastasis, or transaminase >5 times the upper limit of normal with liver metastasis. In clinical trials of the weekly dosage schedule, patients with modestly elevated baseline serum total bilirubin levels (1.0 to 2.0 mg/dL) had a significantly greater likelihood of experiencing first-cycle, grade 3 or 4 neutropenia than those with bilirubin levels that were less than 1.0 mg/dL (50% [19/38] versus 18% [47/226]; p<0.001) [see Dosage and Administration (2.1), Use in Specific Populations (8.7) and Clinical Pharmacology (12.3)] .

6 ADVERSE REACTIONS

6.1 Clinical Studies Experience

Because clinical trials are conducted under widely varying conditions, adverse reaction rates observed in the clinical trials of a drug cannot be directly compared to rates in the clinical trials of another drug and may not reflect the rates observed in clinical practice.

Common adverse reactions (≥30%) observed in combination therapy clinical studies are: nausea, vomiting, abdominal pain, diarrhea, constipation, anorexia, mucositis, neutropenia, leukopenia (including lymphocytopenia), anemia, thrombocytopenia, asthenia, pain, fever, infection, abnormal bilirubin, and alopecia.

Common adverse reactions (≥30%) observed in single agent therapy clinical studies are: nausea, vomiting, abdominal pain, diarrhea, constipation, anorexia, neutropenia, leukopenia (including lymphocytopenia), anemia, asthenia, fever, body weight decreasing, and alopecia.

First-Line Combination Therapy

A total of 955 patients with metastatic colorectal cancer received the recommended regimens of irinotecan in combination with 5-FU/LV, 5-FU/LV alone, or irinotecan alone. In the two phase 3 studies, 370 patients received irinotecan in combination with 5-FU/LV, 362 patients received 5-FU/LV alone, and 223 patients received irinotecan alone [see Dosage and Administration (2)] .

In Study 1, 49 (7.3%) patients died within 30 days of last study treatment: 21 (9.3%) received irinotecan in combination with 5-FU/LV, 15 (6.8%) received 5-FU/LV alone, and 13 (5.8%) received irinotecan alone. Deaths potentially related to treatment occurred in 2 (0.9%) patients who received irinotecan in combination with 5-FU/LV (2 neutropenic fever/sepsis), 3 (1.4%) patients who received 5-FU/LV alone (1 neutropenic fever/sepsis, 1 CNS bleeding during thrombocytopenia, 1 unknown) and 2 (0.9%) patients who received irinotecan alone (2 neutropenic fever). Deaths from any cause within 60 days of first study treatment were reported for 15 (6.7%) patients who received irinotecan in combination with 5-FU/LV, 16 (7.3%) patients who received 5-FU/LV alone, and 15 (6.7%) patients who received irinotecan alone. Discontinuations due to adverse events were reported for 17 (7.6%) patients who received irinotecan in combination with 5FU/LV, 14 (6.4%) patients who received 5-FU/LV alone, and 26 (11.7%) patients who received irinotecan alone.

In Study 2, 10 (3.5%) patients died within 30 days of last study treatment: 6 (4.1%) received irinotecan in combination with 5-FU/LV and 4 (2.8%) received 5-FU/LV alone. There was one potentially treatment-related death, which occurred in a patient who received irinotecan in combination with 5-FU/LV (0.7%, neutropenic sepsis). Deaths from any cause within 60 days of first study treatment were reported for 3 (2.1%) patients who received irinotecan in combination with 5-FU/LV and 2 (1.4%) patients who received 5-FU/LV alone. Discontinuations due to adverse events were reported for 9 (6.2%) patients who received irinotecan in combination with 5FU/LV and 1 (0.7%) patient who received 5-FU/LV alone.

The most clinically significant adverse events for patients receiving irinotecan-based therapy were diarrhea, nausea, vomiting, neutropenia, and alopecia. The most clinically significant adverse events for patients receiving 5-FU/LV therapy were diarrhea, neutropenia, neutropenic fever, and mucositis. In Study 1, grade 4 neutropenia, neutropenic fever (defined as grade 2 fever and grade 4 neutropenia), and mucositis were observed less often with weekly irinotecan/5-FU/LV than with monthly administration of 5-FU/LV.

Tables 5 and 6 list the clinically relevant adverse events reported in Studies 1 and 2, respectively.

Table 5: Study 1: Percent (%) of Patients Experiencing Clinically Relevant Adverse Events in Combination Therapiesa

Adverse Event | Study 1
Adverse Event | Irinotecan + Bolus 5- FU/LV weekly x 4 every 6 weeks N=225 |  | Bolus 5-FU/LV daily x 5 every 4 weeks N=219 |  | Irinotecan weekly x 4 every 6 weeks N=223
Adverse Event | Grade 1 to 4 | Grade 3&4 | Grade 1 to 4 | Grade 3&4 | Grade 1 to 4 | Grade 3&4
TOTAL Adverse Events | 100 | 53.3 | 100 | 45.7 | 99.6 | 45.7
GASTROINTESTINAL Diarrhea Late grade 3 grade 4 Early Nausea Abdominal pain Vomiting Anorexia Constipation Mucositis | 84.9 -- -- 45.8 79.1 63.1 60.4 34.2 41.3 32.4 | 22.7 15.1 7.6 4.9 15.6 14.6 9.7 5.8 3.1 2.2 | 69.4 -- -- 31.5 67.6 50.2 46.1 42.0 31.5 76.3 | 13.2 5.9 7.3 1.4 8.2 11.5 4.1 3.7 1.8 16.9 | 83.0 -- -- 43.0 81.6 67.7 62.8 43.9 32.3 29.6 | 31.0 18.4 12.6 6.7 16.1 13.0 12.1 7.2 0.4 2.2
HEMATOLOGIC Neutropenia grade 3 grade 4 Leukopenia Anemia Neutropenic fever Thrombocytopenia Neutropenic infection | 96.9 -- -- 96.9 96.9 -- 96.0 -- | 53.8 29.8 24.0 37.8 8.4 7.1 2.6 1.8 | 98.6 -- -- 98.6 98.6 -- 98.6 -- | 66.7 23.7 42.5 23.3 5.5 14.6 2.7 0 | 96.4 -- --‑ 96.4 96.9 -- 96.0 -- | 31.4 19.3 12.1 21.5 4.5 5.8 1.7 2.2
BODY AS A WHOLE Asthenia Pain Fever Infection | 70.2 30.7 42.2 22.2 | 19.5 3.1 1.7 0 | 64.4 26.9 32.4 16.0 | 11.9 3.6 3.6 1.4 | 69.1 22.9 43.5 13.9 | 13.9 2.2 0.4 0.4
METABOLIC & NUTRITIONAL
Bilirubin | 87.6 | 7.1 | 92.2 | 8.2 | 83.9 | 7.2
DERMATOLOGIC Exfoliative dermatitis Rash Alopeciab | 0.9 19.1 43.1 | 0 0 -- | 3.2 26.5 26.5 | 0.5 0.9 -- | 0 14.3 46.1 | 0 0.4 --
RESPIRATORY Dyspnea Cough Pneumonia | 27.6 26.7 6.2 | 6.3 1.3 2.7 | 16.0 18.3 1.4 | 0.5 0 1.0 | 22.0 20.2 3.6 | 2.2 0.4 1.3
NEUROLOGIC Dizziness Somnolence Confusion | 23.1 12.4 7.1 | 1.3 1.8 1.8 | 16.4 4.6 4.1 | 0 1.8 0 | 21.1 9.4 2.7 | 1.8 1.3 0
CARDIOVASCULAR Vasodilatation Hypotension Thromboembolic eventsc | 9.3 5.8 9.3 | 0.9 1.3 -- | 5.0 2.3 11.4 | 0 0.5 -- | 9.0 5.8 5.4 | 0 1.7 --

aSeverity of adverse events based on NCI CTC (version 1.0)

bComplete hair loss = Grade 2

cIncludes angina pectoris, arterial thrombosis, cerebral infarct, cerebrovascular accident, deep thrombophlebitis, embolus lower extremity, heart arrest, myocardial infarct, myocardial ischemia, peripheral vascular disorder, pulmonary embolus, sudden death, thrombophlebitis, thrombosis, vascular disorder.

Table 6: Study 2: Percent (%) of Patients Experiencing Clinically Relevant Adverse Events in Combination Therapiesa

Adverse Event | Study 2
Adverse Event | Irinotecan + 5-FU/LV infusional days 1&2 every 2 weeks N= 145 |  | 5-FU/LV infusional days 1&2 every 2 weeks N= 143
Adverse Event | Grades 1 to 4 | Grades 3&4 | Grades 1 to 4 | Grades 3&4
TOTAL Adverse Events | 100 | 72.4 | 100 | 39.2
GASTROINTESTINAL Diarrhea late grade 3 grade 4 Cholinergic syndromeb Nausea Abdominal pain Vomiting Anorexia Constipation Mucositis | 72.4 -- -- 28.3 66.9 17.2 44.8 35.2 30.3 40.0 | 14.4 10.3 4.1 1.4 2.1 2.1 3.5 2.1 0.7 4.1 | 44.8 -- -- 0.7 55.2 16.8 32.2 18.9 25.2 28.7 | 6.3 4.2 2.1 0 3.5 0.7 2.8 0.7 1.4 2.8
HEMATOLOGIC Neutropenia grade 3 grade 4 Leukopenia Anemia Neutropenic fever Thrombocytopenia Neutropenic infection | 82.5 -- -‑- 81.3 97.2 -‑- 32.6 -‑- | 46.2 36.4 9.8 17.4 2.1 3.4 0 2.1 | 47.9 -- -‑- 42.0 90.9 -‑- 32.2 -‑- | 13.4 12.7 0.7 3.5 2.1 0.7 0 0
BODY AS A WHOLE Asthenia Pain Fever Infection | 57.9 64.1 22.1 35.9 | 9.0 9.7 0.7 7.6 | 48.3 61.5 25.9 33.6 | 4.2 8.4 0.7 3.5
METABOLIC AND NUTRITIONAL Bilirubin | 19.1 | 3.5 | 35.9 | 10.6
DERMATOLOGIC Hand and foot syndrome Cutaneous signs Alopeciac | 10.3 17.2 56.6 | 0.7 0.7 -- | 12.6 20.3 16.8 | 0.7 0 --
RESPIRATORY Dyspnea | 9.7 | 1.4 | 4.9 | 0
CARDIOVASCULAR Hypotension Thromboembolic eventsd | 3.4 11.7 | 1.4 -- | 0.7 5.6 | 0 --

aSeverity of adverse events based on NCI CTC (version 1.0)

bIncludes rhinitis, increased salivation, miosis, lacrimation, diaphoresis, flushing, abdominal cramping or diarrhea (occurring during or shortly after infusion of irinotecan)

cComplete hair loss = Grade 2

dIncludes angina pectoris, arterial thrombosis, cerebral infarct, cerebrovascular accident, deep thrombophlebitis, embolus lower extremity, heart arrest, myocardial infarct, myocardial ischemia, peripheral vascular disorder, pulmonary embolus, sudden death, thrombophlebitis, thrombosis, vascular disorder.

Second-Line Single-Agent Therapy

Weekly Dosage Schedule
In three clinical studies evaluating the weekly dosage schedule, 304 patients with metastatic carcinoma of the colon or rectum that had recurred or progressed following 5-FU-based therapy were treated with irinotecan hydrochloride injection. Seventeen of the patients died within 30 days of the administration of irinotecan hydrochloride injection; in five cases (1.6%, 5/304), the deaths were potentially drug-related. One of the patients died of neutropenic sepsis without fever. Neutropenic fever occurred in nine (3.0%) other patients; these patients recovered with supportive care.

One hundred nineteen (39.1%) of the 304 patients were hospitalized because of adverse events; 81 (26.6%) patients were hospitalized for events judged to be related to administration of irinotecan hydrochloride injection. The primary reasons for drug-related hospitalization were diarrhea, with or without nausea and/or vomiting (18.4%); neutropenia/leukopenia, with or without diarrhea and/or fever (8.2%); and nausea and/or vomiting (4.9%).

The first dose of at least one cycle of irinotecan hydrochloride injection was reduced for 67% of patients who began the studies at the 125-mg/m^2starting dose. Within-cycle dose reductions were required for 32% of the cycles initiated at the 125-mg/m^2dose level. The most common reasons for dose reduction were late diarrhea, neutropenia, and leukopenia. Thirteen (4.3%) patients discontinued treatment with irinotecan hydrochloride injection because of adverse events. The adverse events in Table 7 are based on the experience of the 304 patients enrolled in the three studies described in Clinical Studies (14.1).
Table 7: Adverse Events Occurring in >10% of 304 Previously Treated Patients with Metastatic Carcinoma of the Colon or Rectuma

Body System & Event | % of Patients Reporting
Body System & Event | NCI Grades 1 to 4 | NCI Grades 3 & 4
GASTROINTESTINAL Diarrhea (late)b 7 to 9 stools/day (grade 3) ≥10 stools/day (grade 4) Nausea Vomiting Anorexia Diarrhea (early)c Constipation Flatulence Stomatitis Dyspepsia | 88 __ __ 86 67 55 51 30 12 12 10 | 31 (16) (14) 17 12 6 8 2 0 1 0
HEMATOLOGIC Leukopenia Anemia Neutropenia 500 to <1000/mm^3(grade 3) <500/mm^3(grade 4) | 63 60 54 __ __ | 28 7 26 (15) (12)
BODY AS A WHOLE Asthenia Abdominal cramping/pain Fever Pain Headache Back pain Chills Minor infectiond Edema Abdominal enlargement | 76 57 45 24 17 14 14 14 10 10 | 12 16 1 2 1 2 0 0 1 0
METABOLIC AND NUTRITIONAL ↓ Body weight Dehydration ↑ Alkaline phosphatase ↑ SGOT | 30 15 13 10 | 1 4 4 1
DERMATOLOGIC Alopecia Sweating Rash | 60 16 13 | NAe 0 1
RESPIRATORY Dyspnea ↑ Coughing Rhinitis | 22 17 16 | 4 0 0
NEUROLOGIC Insomnia Dizziness | 19 15 | 0 0
CARDIOVASCULAR Vasodilation (flushing) | 11 | 0

aSeverity of adverse events based on NCI CTC (version 1.0)
bOccurring >24 hours after administration of irinotecan hydrochloride injection
cOccurring ≤24 hours after administration of irinotecan hydrochloride injection
dPrimarily upper respiratory infections
eNot applicable; complete hair loss = NCI grade 2

Once-Every-3-Week Dosage Schedule
A total of 535 patients with metastatic colorectal cancer whose disease had recurred or progressed following prior 5-FU therapy participated in the two phase 3 studies: 316 received irinotecan, 129 received 5-FU, and 90 received best supportive care. Eleven (3.5%) patients treated with irinotecan died within 30 days of treatment. In three cases (1%, 3/316), the deaths were potentially related to irinotecan treatment and were attributed to neutropenic infection, grade 4 diarrhea, and asthenia, respectively. One (0.8%, 1/129) patient treated with 5-FU died within 30 days of treatment; this death was attributed to grade 4 diarrhea.

Hospitalizations due to serious adverse events occurred at least once in 60% (188/316) of patients who received irinotecan, 63% (57/90) who received best supportive care, and 39% (50/129) who received 5-FU-based therapy. Eight percent of patients treated with irinotecan and 7% treated with 5-FU-based therapy discontinued treatment due to adverse events.

Of the 316 patients treated with irinotecan, the most clinically significant adverse events (all grades, 1 to 4) were diarrhea (84%), alopecia (72%), nausea (70%), vomiting (62%), cholinergic symptoms (47%), and neutropenia (30%). Table 8 lists the grade 3 and 4 adverse events reported in the patients enrolled to all treatment arms of the two studies described in Clinical Studies (14.1).

Table 8: Percent Of Patients Experiencing Grade 3 & 4 Adverse Events In Comparative Studies Of Once-Every-3-Week Irinotecan Therapya

Adverse Event | Study 1 |  | Study 2
Adverse Event | Irinotecan N=189 | BSCb N=90 | Irinotecan N=127 | 5-FU N=129
TOTAL Grade 3/4 Adverse Events | 79 | 67 | 69 | 54
GASTROINTESTINAL Diarrhea Vomiting Nausea Abdominal pain Constipation Anorexia Mucositis | 22 14 14 14 10 5 2 | 6 8 3 16 8 7 1 | 22 14 11 9 8 6 2 | 11 5 4 8 6 4 5
HEMATOLOGIC Leukopenia/Neutropenia Anemia Hemorrhage Thrombocytopenia Infection without grade 3/4 neutropenia with grade 3/4 neutropenia Fever without grade 3/4 neutropenia with grade 3/4 neutropenia | 22 7 5 1 8 1 2 2 | 0 6 3 0 3 0 1 0 | 14 6 1 4 1 2 2 4 | 2 3 3 2 4 0 0 2
BODY AS A WHOLE Pain Asthenia | 19 15 | 22 19 | 17 13 | 13 12
METABOLIC AND NUTRITIONAL Hepaticc | 9 | 7 | 9 | 6
DERMATOLOGIC Hand and foot syndrome Cutaneous signsd | 0 2 | 0 0 | 0 1 | 5 3
RESPIRATORYe | 10 | 8 | 5 | 7
NEUROLOGICf | 12 | 13 | 9 | 4
CARDIOVASCULARg | 9 | 3 | 4 | 2
OTHERh | 32 | 28 | 12 | 14

aSeverity of adverse events based on NCI CTC (version 1.0)
bBSC = best supportive care
cHepatic includes events such as ascites and jaundice
dCutaneous signs include events such as rash
eRespiratory includes events such as dyspnea and cough
fNeurologic includes events such as somnolence
gCardiovascular includes events such as dysrhythmias, ischemia, and mechanical cardiac dysfunction
hOther includes events such as accidental injury, hepatomegaly, syncope, vertigo, and weight loss
The incidence of akathisia in clinical trials of the weekly dosage schedule was greater (8.5%, 4/47 patients) when prochlorperazine was administered on the same day as irinotecan hydrochloride injection than when these drugs were given on separate days (1.3%, 1/80 patients). The 8.5% incidence of akathisia, however, is within the range reported for use of prochlorperazine when given as a premedication for other chemotherapies.

6.2 Postmarketing Experience

The following adverse reactions have been identified during post approval use of irinotecan hydrochloride injection. Because these reactions are reported voluntarily from a population of uncertain size, it is not always possible to reliably estimate their frequency or establish a causal relationship to drug exposure.

Myocardial ischemic events have been observed following irinotecan hydrochloride injection therapy. Thromboembolic events have been observed in patients receiving irinotecan hydrochloride injection.

Symptomatic pancreatitis, asymptomatic pancreatic enzyme elevation have been reported. Increases in serum levels of transaminases (i.e., AST and ALT) in the absence of progressive liver metastasis have been observed.

Hyponatremia, mostly with diarrhea and vomiting, has been reported.

Transient dysarthria has been reported in patients treated with irinotecan hydrochloride injection; in some cases, the event was attributed to the cholinergic syndrome observed during or shortly after infusion of irinotecan.

Interaction between irinotecan and neuromuscular blocking agents cannot be ruled out. Irinotecan has anticholinesterase activity, which may prolong the neuromuscular blocking effects of suxamethonium and the neuromuscular blockade of non-depolarizing drugs may be antagonized.

Infections: fungal and viral infections have been reported.

7 DRUG INTERACTIONS

7.1 5-Fluorouracil (5-FU) and Leucovorin (LV)

In a phase 1 clinical study involving irinotecan, 5-fluorouracil (5-FU), and leucovorin (LV) in 26 patients with solid tumors, the disposition of irinotecan was not substantially altered when the drugs were co-administered. Although the Cmaxand AUC0 to 24of SN-38, the active metabolite, were reduced (by 14% and 8%, respectively) when irinotecan was followed by 5-FU and LV administration compared with when irinotecan was given alone, this sequence of administration was used in the combination trials and is recommended [see Dosage and Administration (2)] . Formal i n vivo or in vitrodrug interaction studies to evaluate the influence of irinotecan on the disposition of 5-FU and LV have not been conducted

7.2 Strong CYP3A4 Inducers

Exposure to irinotecan or its active metabolite SN-38 is substantially reduced in adult and pediatric patients concomitantly receiving the CYP3A4 enzyme-inducing anticonvulsants phenytoin, phenobarbital, carbamazepine, or St. John's wort. The appropriate starting dose for patients taking these or other strong inducers such as rifampin and rifabutin has not been defined. Consider substituting non-enzyme inducing therapies at least 2 weeks prior to initiation of irinotecan hydrochloride injection therapy. Do not administer strong CYP3A4 inducers with irinotecan hydrochloride injection unless there are no therapeutic alternatives.

7.3 Strong CYP3A4 or UGT1A1 Inhibitors

Irinotecan and its active metabolite, SN-38, are metabolized via the human cytochrome P450 3A4 isoenzyme (CYP3A4) and uridine diphosphate-glucuronosyl transferase 1A1 (UGT1A1), respectively, [see Clinical Pharmacology (12.3)]. Patients receiving concomitant ketoconazole, a CYP3A4 and UGT1A1 inhibitor, have increased exposure to irinotecan and its active metabolite SN-38. Coadministration of irinotecan hydrochloride injection with other inhibitors of CYP3A4 (e.g., clarithromycin, indinavir, itraconazole, lopinavir, nefazodone, nelfinavir, ritonavir, saquinavir, telaprevir, voriconazole) or UGT1A1 (e.g., atazanavir, gemfibrozil, indinavir) may increase systemic exposure to irinotecan or SN-38. Discontinue strong CYP3A4 inhibitors at least 1 week prior to starting irinotecan hydrochloride injection therapy. Do not administer strong CYP3A4 or UGT1A1 inhibitors with irinotecan hydrochloride injection unless there are no therapeutic alternatives.

8 USE IN SPECIFIC POPULATIONS

8.1 Pregnancy

Risk Summary

Based on findings from animal studies and its mechanism of action, irinotecan hydrochloride injection can cause fetal harm when administered to a pregnant woman [see Clinical Pharmacology (12.1)]. Available postmarketing and published data reporting the use of irinotecan hydrochloride injection in pregnant women, are insufficient and confounded by the concomitant use of other cytotoxic drugs, to evaluate for any drug-associated risk for major birth defects, miscarriage, or adverse maternal or fetal outcomes. In animal studies, intravenous administration of irinotecan to rats and rabbits during the period of organogenesis resulted in embryofetal mortality and teratogenicity in pregnant animals at exposures lower than the human exposure based on AUC at the clinical dose of 125 mg/m^2 (see Data).Advise pregnant women of the potential risk to a fetus.

In the U.S. general population, the estimated background risk of major birth defects and miscarriage in clinically recognized pregnancies is 2 to 4% and 15 to 20%, respectively.

Data

Animal Data

Radioactivity related to^14C-irinotecan crosses the placenta of rats following intravenous administration. Intravenous administration of irinotecan to rats at a dose of 6 mg/kg/day (approximately 0.2 times the clinical exposure (AUC) at the 125 mg/m^2dose based on exposure data from a separate rat study) during the period of organogenesis resulted in increased post-implantation loss and decreased numbers of live fetuses; at doses ≥ 1.2 mg/kg/day (approximately 0.03 times the clinical exposure (AUC) at the 125 mg/m^2dose based on exposure data from a separate rat study) there were increases in a variety of external, visceral, and skeletal abnormalities. Administration of irinotecan to pregnant rabbits at a dose of 6 mg/kg (approximately half of the clinical dose of 125 mg/m^2based on BSA) resulted in similar findings to those in rats, with increased post-implantation loss, decreased live fetuses, and increased external, visceral, and skeletal abnormalities.

Irinotecan administered to rat dams for the period following organogenesis through weaning at doses of 6 mg/kg/day caused decreased learning ability and decreased female body weights in the offspring.

8.2 Lactation

Risk Summary

Irinotecan and its metabolites are present in human milk. There is no information regarding the effects of irinotecan on the breastfed infant, or on milk production. Because of the potential for serious adverse reactions from irinotecan hydrochloride injection in the breastfed child, advise lactating women not to breastfeed during treatment with irinotecan hydrochloride injection and for 7 days after the final dose.

8.3 Females and Males of Reproductive Potential

Pregnancy Testing
Verify the pregnancy status in female patients of reproductive potential prior to initiating irinotecan hydrochloride injection.

Contraception
Irinotecan hydrochloride injection can cause fetal harm when administered to a pregnant woman.

Females

Advise female patients of reproductive potential to use effective contraception during treatment and for 6 months after the final dose of irinotecan hydrochloride injection [see Use in Specific Populations (8.1)and Nonclinical Toxicology (13.1)].

Males

Due to the potential for genotoxicity, advise male patients with female partners of reproductive potential to use condoms during treatment and for 3 months after the final dose of irinotecan hydrochloride injection [see Nonclinical Toxicology (13.1)].

Infertility
Females

Based on postmarketing reports, female fertility may be impaired by treatment with irinotecan hydrochloride injection. Menstrual dysfunction has been reported following irinotecan hydrochloride injection administration.

Males

Based on findings from animal studies, male fertility may be impaired by treatment with irinotecan hydrochloride injection [see Nonclinical Toxicology (13.1)].

8.4 Pediatric Use

The effectiveness of irinotecan in pediatric patients has not been established. Results from two open-label, single arm studies were evaluated. One hundred and seventy children with refractory solid tumors were enrolled in one phase 2 trial in which 50 mg/m^2of irinotecan was infused for 5 consecutive days every 3 weeks. Grade 3-4 neutropenia was experienced by 54 (31.8%) patients. Neutropenia was complicated by fever in 15 (8.8%) patients. Grade 3-4 diarrhea was observed in 35 (20.6%) patients. This adverse event profile was comparable to that observed in adults. In the second phase 2 trial of 21 children with previously untreated rhabdomyosarcoma, 20 mg/m^2of irinotecan was infused for 5 consecutive days on weeks 0, 1, 3 and 4. This single agent therapy was followed by multimodal therapy. Accrual to the single agent irinotecan phase was halted due to the high rate (28.6%) of progressive disease and the early deaths (14%). The adverse event profile was different in this study from that observed in adults; the most significant grade 3 or 4 adverse events were dehydration experienced by 6 patients (28.6%) associated with severe hypokalemia in 5 patients (23.8%) and hyponatremia in 3 patients (14.3%); in addition Grade 3-4 infection was reported in 5 patients (23.8%) (across all courses of therapy and irrespective of causal relationship).

Pharmacokinetic parameters for irinotecan and SN-38 were determined in 2 pediatric solid-tumor trials at dose levels of 50 mg/m^2(60-min infusion, n=48) and 125 mg/m^2(90-min infusion, n=6). Irinotecan clearance (mean ± S.D.) was 17.3 ± 6.7 L/h/m^2for the 50mg/m^2dose and 16.2 ± 4.6 L/h/m^2for the 125 mg/m^2dose, which is comparable to that in adults. Dose-normalized SN-38 AUC values were comparable between adults and children. Minimal accumulation of irinotecan and SN-38 was observed in children on daily dosing regimens [daily x 5 every 3 weeks or (daily x 5) x 2 weeks every 3 weeks].

8.5 Geriatric Use

Patients greater than 65 years of age should be closely monitored because of a greater risk of early and late diarrhea in this population [see Clinical Pharmacology (12.3)and Adverse Reactions (6.1)]. The starting dose of irinotecan hydrochloride injection in patients 70 years and older for the once-every-3-week-dosage schedule should be 300 mg/m^2 [see Clinical Pharmacology (12.3)and Dosage and Administration (2)].

The frequency of grade 3 and 4 late diarrhea by age was significantly greater in patients ≥65 years than in patients <65 years (40% [53/133] versus 23% [40/171]; p=0.002). In another study of 183 patients treated on the weekly schedule, the frequency of grade 3 or 4 late diarrhea in patients ≥65 years of age was 28.6% [26/91] and in patients <65 years of age was 23.9% [22/92].

8.6 Renal Impairment

The influence of renal impairment on the pharmacokinetics of irinotecan has not been evaluated. Therefore, use caution in patients with impaired renal function. Irinotecan hydrochloride injection is not recommended for use in patients on dialysis.

8.7 Hepatic Impairment

Irinotecan clearance is diminished in patients with hepatic impairment while exposure to the active metabolite SN-38 is increased relative to that in patients with normal hepatic function. The magnitude of these effects is proportional to the degree of liver impairment as measured by elevations in total bilirubin and transaminase concentrations. Therefore, use caution when administering irinotecan hydrochloride injection to patients with hepatic impairment. The tolerability of irinotecan in patients with hepatic dysfunction (bilirubin greater than 2 mg/dl) has not been assessed sufficiently, and no recommendations for dosing can be made [see Dosage and Administration (2.1), Warnings and Precautions (5.10) and Clinical Pharmacology (12.3)] .

10 OVERDOSAGE

In U.S. phase 1 trials, single doses of up to 345 mg/m^2of irinotecan were administered to patients with various cancers. Single doses of up to 750 mg/m^2of irinotecan have been given in non-U.S. trials. The adverse events in these patients were similar to those reported with the recommended dosage and regimen. There have been reports of overdosage at doses up to approximately twice the recommended therapeutic dose, which may be fatal. The most significant adverse reactions reported were severe neutropenia and severe diarrhea. There is no known antidote for overdosage of irinotecan hydrochloride injection. Maximum supportive care should be instituted to prevent dehydration due to diarrhea and to treat any infectious complications.

11 DESCRIPTION

Irinotecan hydrochloride injection, USP is an antineoplastic agent of the topoisomerase I inhibitor class.

Irinotecan hydrochloride injection, USP is supplied as a sterile, pale yellow, clear, aqueous solution. Each milliliter of solution contains 20 mg of irinotecan hydrochloride (on the basis of the trihydrate salt), 45 mg of sorbitol, NF, and 0.9 mg of lactic acid, USP. The pH of the solution has been adjusted to 3.5 (range, 3.0 to 3.8) with sodium hydroxide or hydrochloric acid. Irinotecan hydrochloride injection, USP is intended for dilution with 5% Dextrose Injection, USP (D5W), or 0.9% Sodium Chloride Injection, USP, prior to intravenous infusion. The preferred diluent is 5% Dextrose Injection, USP.

Irinotecan hydrochloride is a semisynthetic derivative of camptothecin, an alkaloid extract from plants such as Camptotheca acuminataor is chemically synthesized.

The chemical name is (S)-4,11-diethyl-3,4,12,14-tetrahydro-4-hydroxy-3,14-dioxo1 H-pyrano[3’,4’:6,7]-indolizino[1,2-b]quinolin-9-yl-[1,4’bipiperidine]-1’-carboxylate, monohydrochloride, trihydrate. Its empirical formula is C33H38N4O6•HCl•3H2O and molecular weight is 677.19. It is slightly soluble in water and organic solvents. Its structural formula is as follows:

12 CLINICAL PHARMACOLOGY

12.1 Mechanism of Action

Irinotecan is a derivative of camptothecin. Camptothecins interact specifically with the enzyme topoisomerase I, which relieves torsional strain in DNA by inducing reversible single-strand breaks. Irinotecan and its active metabolite SN-38 bind to the topoisomerase I-DNA complex and prevent religation of these single-strand breaks. Current research suggests that the cytotoxicity of irinotecan is due to double-strand DNA damage produced during DNA synthesis when replication enzymes interact with the ternary complex formed by topoisomerase I, DNA, and either irinotecan or SN-38. Mammalian cells cannot efficiently repair these double-strand breaks.

12.2 Pharmacodynamics

Irinotecan serves as a water-soluble precursor of the lipophilic metabolite SN-38. SN-38 is formed from irinotecan by carboxylesterase-mediated cleavage of the carbamate bond between the camptothecin moiety and the dipiperidino side chain. SN-38 is approximately 1000 times as potent as irinotecan as an inhibitor of topoisomerase I purified from human and rodent tumor cell lines. In vitrocytotoxicity assays show that the potency of SN-38 relative to irinotecan varies from 2-to 2000-fold; however, the plasma area under the concentration versus time curve (AUC) values for SN-38 are 2% to 8% of irinotecan and SN-38 is 95% bound to plasma proteins compared to approximately 50% bound to plasma proteins for irinotecan [see Clinical Pharmacology (12.3)]. The precise contribution of SN-38 to the activity of irinotecan is thus unknown. Both irinotecan and SN-38 exist in an active lactone form and an inactive hydroxy acid anion form. A pH-dependent equilibrium exists between the two forms such that an acid pH promotes the formation of the lactone, while a more basic pH favors the hydroxy acid anion form.

Administration of irinotecan has resulted in antitumor activity in mice bearing cancers of rodent origin and in human carcinoma xenografts of various histological types.

12.3 Pharmacokinetics

After intravenous infusion of irinotecan in humans, irinotecan plasma concentrations decline in a multiexponential manner, with a mean terminal elimination half-life of about 6 to 12 hours. The mean terminal elimination half-life of the active metabolite SN-38 is about 10 to 20 hours. The half-lives of the lactone (active) forms of irinotecan and SN-38 are similar to those of total irinotecan and SN-38, as the lactone and hydroxy acid forms are in equilibrium.

Over the recommended dose range of 50 to 350 mg/m^2, the AUC of irinotecan increases linearly with dose; the AUC of SN-38 increases less than proportionally with dose. Maximum concentrations of the active metabolite SN-38 are generally seen within 1 hour following the end of a 90-minute infusion of irinotecan. Pharmacokinetic parameters for irinotecan and SN-38 following a 90-minute infusion of irinotecan at dose levels of 125 and 340 mg/m^2determined in two clinical studies in patients with solid tumors are summarized in Table 9:
Table 9. Summary of Mean (±Standard Deviation) Irinotecan and SN-38 Pharmacokinetic Parameters in Patients with Solid Tumors

Dose (mg/m^2) | Irinotecan |  |  |  |  | SN-38
Dose (mg/m^2) | Cmax(ng/mL) | AUC0-24(ng·h/mL) | t1/2(h) | Vz(L/m^2) | CL (L/h/m^2) | Cmax(ng/mL) | AUC0-24(ng·h/mL) | t1/2(h)
125 (N=64) | 1,660 ±797 | 10,200 ±3,270 | 5.8a ±0.7 | 110 ±48.5 | 13.3 ±6.01 | 26.3 ±11.9 | 229 ±108 | 10.4a ±3.1
340 (N=6) | 3,392 ±874 | 20,604 ±6,027 | 11.7b ±1.0 | 234 ±69.6 | 13.9 ±4.0 | 56.0 ±28.2 | 474 ±245 | 21.0b ±4.3

Cmax- Maximum plasma concentration
AUC0-24- Area under the plasma concentration-time curve from time
0 to 24 hours after the end of the 90-minute infusion
t1/2- Terminal elimination half-life
Vz -Volume of distribution of terminal elimination phase
CL -Total systemic clearance
aPlasma specimens collected for 24 hours following the end of the 90-minute infusion.
bPlasma specimens collected for 48 hours following the end of the 90-minute infusion. Because of the longer collection period, these values provide a more accurate reflection of the terminal elimination half-lives of irinotecan and SN-38.
Distribution
Irinotecan exhibits moderate plasma protein binding (30% to 68% bound). SN-38 is highly bound to human plasma proteins (approximately 95% bound). The plasma protein to which irinotecan and SN-38 predominantly binds is albumin.

Metabolism
Irinotecan is subject to extensive metabolic conversion by various enzyme systems, including esterases that form an active metabolite SN-38, and UGT1A1 which mediates the glucuronidation of SN-38 to form an inactive metabolite. SN-38 glucuronide had 1/50 to 1/100 the activity of SN-38. Patients who are homozygous for either the UGT1A1*28 or *6 alleles, or who are compound heterozygous for these alleles, have higher SN-38 AUC than patients with the wild-type UGT1A1 alleles [see Dosage and Administration (2.3), Warnings and Precautions (5.3), and Clinical Pharmacology (12.5)].

Excretion
The disposition of irinotecan has not been fully elucidated in humans. The urinary excretion of irinotecan is 11% to 20%; SN-38, <1%; and SN-38 glucuronide, 3%. The cumulative biliary and urinary excretion of irinotecan and its metabolites (SN-38 and SN-38 glucuronide) over a period of 48 hours following administration of irinotecan in two patients ranged from approximately 25% (100 mg/m^2) to 50% (300 mg/m^2).

Specific Population

Geriatric Patients
The pharmacokinetics of irinotecan administered using the weekly schedule was evaluated in a study of 183 patients that was prospectively designed to investigate the effect of age on irinotecan toxicity. Results from this trial indicate that there are no differences in the pharmacokinetics of irinotecan, SN-38, and SN-38 glucuronide in patients <65 years of age compared with patients ≥65 years of age. In a study of 162 patients that was not prospectively designed to investigate the effect of age, small (less than 18%) but statistically significant differences in dose-normalized irinotecan pharmacokinetic parameters in patients <65 years of age compared to patients ≥65 years of age were observed. Although dose-normalized AUC0-24for SN-38 in patients ≥65 years of age was 11% higher than in patients <65 years of age, this difference was not statistically significant. No change in the starting dose is recommended for geriatric patients receiving the weekly dosage schedule of irinotecan [see Dosage and Administration (2)].

Male and Female Patients
The pharmacokinetics of irinotecan do not appear to be influenced by gender.

Racial and Ethical Groups
The influence of race on the pharmacokinetics of irinotecan has not been evaluated.

Patients with Renal Impairment

The influence of renal impairment on the pharmacokinetics of irinotecan has not been evaluated.

Patients with Hepatic Impairment

Irinotecan clearance is diminished in patients with hepatic impairment while exposure to the active metabolite SN-38 is increased relative to that in patients with normal hepatic function. The magnitude of these effects is proportional to the degree of liver impairment as measured by elevations in total bilirubin and transaminase concentrations. However, the tolerability of irinotecan in patients with hepatic dysfunction (bilirubin greater than 2 mg/dl) has not been assessed sufficiently.

Drug Interaction Studies

Clinical Studies and Model-Informed Approaches

Dexamethasone, a moderate CYP3A4 inducer, does not appear to alter the pharmacokinetics of irinotecan.

In Vitro Studies

Irinotecan and the metabolites SN-38 and aminopentane carboxylic acid (APC) do not inhibit cytochrome P-450 isozymes.

12.5 Pharmacogenomics

The active metabolite SN-38 is further metabolized via UGT1A1. Genetic variants of the UGT1A1 gene such as the UGT1A1*28 [(TA)7] and *6 alleles lead to reduced UGT1A1 enzyme expression or activity and decreased function to a similar extent.

Individuals who are homozygous or compound (double) heterozygous for these alleles (e.g., *28/*28, *6/*6, *6/*28) are UGT1A1 poor metabolizers and are at increased risk for severe or life-threatening neutropenia from irinotecan hydrochloride due to elevated systemic exposure to SN-38.

The UGT1A1*6/*6 genotype should not be confused with 6/6 genotype, which is sometimes used to represent the genotype of individuals who are wild type for UGT1A1*28. Individuals who are heterozygous for either the UGT1A1*28 or *6 alleles (*1/*6, *1/*28) are UGT1A1 intermediate metabolizers and may also have an increased risk of severe or life-threatening neutropenia [see Dosage and Administration (2.3), Warnings and Precautions (5.3), and Clinical Pharmacology (12.3)].

Published studies have shown that individuals with UGT1A1*28 and *6 alleles may be at an increased risk of severe diarrhea. The risk evidence appears greater in UGT1A1*28 and *6 homozygous patients and in those taking irinotecan doses > 125 mg/m2 [see Warnings and Precautions (5.1)].

UGT1A1*28 and *6 alleles occur at various frequencies in different populations. Approximately 20% of Black or African American, 10% of White, and 2% of East Asian individuals are homozygous for the UGT1A1*28 allele. Approximately 2-6 % of East Asian individuals are homozygous for the UGT1A1*6 allele. The UGT1A1*6 allele is uncommon in Black or African American or in White individuals. Decreased function alleles other than UGT1A1*28 and *6 may be present in certain populations.

13 NONCLINICAL TOXICOLOGY

13.1 Carcinogenesis, Mutagenesis, Impairment of Fertility

Long-term carcinogenicity studies with irinotecan were not conducted. Rats were, however, administered intravenous doses of 2 mg/kg or 25 mg/kg irinotecan once per week for 13 weeks (in separate studies, the 25 mg/kg dose produced an irinotecan Cmaxand AUC that were about 7.0 times and 1.3 times the respective values in patients administered 125 mg/m^2weekly) and were then allowed to recover for 91 weeks. Under these conditions, there was a significant linear trend with dose for the incidence of combined uterine horn endometrial stromal polyps and endometrial stromal sarcomas. Irinotecan was clastogenic both in vitro (chromosome aberrations in Chinese hamster ovary cells) and in vivo(micronucleus test in mice). Neither irinotecan nor its active metabolite SN-38 was mutagenic in the in vitroAmes assay.

No significant adverse effects on fertility and general reproductive performance were observed after intravenous administration of irinotecan in doses of up to 6 mg/kg/day to rats and rabbits; however, atrophy of male reproductive organs was observed after multiple daily irinotecan doses both in rodents at 20 mg/kg and in dogs at 0.4 mg/kg. In separate studies in rodents, this dose produced an irinotecan Cmaxand AUC about 5 and 1 times, respectively, of the corresponding values in patients administered 125 mg/m^2weekly. In dogs this dose produced an irinotecan Cmaxand AUC about one-half and 1/15th, respectively, of the corresponding values in patients administered 125 mg/m^2weekly.

14 CLINICAL STUDIES

Irinotecan has been studied in clinical trials in combination with 5-fluorouracil (5-FU) and leucovorin (LV) and as a single agent [see Dosage and Administration (2)]. When given as a component of combination-agent treatment, irinotecan was either given with a weekly schedule of bolus 5-FU/LV or with an every-2-week schedule of infusional 5-FU/LV. Weekly and once-every-3-week dosage schedules were used for the single-agent irinotecan studies. Clinical studies of combination and single-agent use are described below.

14.1 Metastatic Colorectal Cancer

First Line Therapy in Combination with 5-FU/LV: Studies 1 and 2

Two phase 3, randomized, controlled, multinational clinical trials support the use of irinotecan hydrochloride injection as first-line treatment of patients with metastatic carcinoma of the colon or rectum. In each study, combinations of irinotecan with 5-FU and LV were compared with 5-FU and LV alone. Study 1 compared combination irinotecan/bolus 5-FU/LV therapy given weekly with a standard bolus regimen of 5-FU/LV alone given daily for 5 days every 4 weeks; an irinotecan-alone treatment arm given on a weekly schedule was also included. Study 2 evaluated two different methods of administering infusional 5-FU/LV, with or without irinotecan. In both studies, concomitant medications such as antiemetics, atropine, and loperamide were given to patients for prophylaxis and/or management of symptoms from treatment. In Study 2, a 7-day course of fluoroquinolone antibiotic prophylaxis was given in patients whose diarrhea persisted for greater than 24 hours despite loperamide or if they developed a fever in addition to diarrhea. Treatment with oral fluoroquinolone was also initiated in patients who developed an absolute neutrophil count (ANC) <500/mm^3, even in the absence of fever or diarrhea. Patients in both studies also received treatment with intravenous antibiotics if they had persistent diarrhea or fever or if ileus developed.

In both studies, the combination of irinotecan/5-FU/LV therapy resulted in significant improvements in objective tumor response rates, time to tumor progression, and survival when compared with 5-FU/LV alone. These differences in survival were observed in spite of second-line therapy in a majority of patients on both arms, including crossover to irinotecan-containing regimens in the control arm. Patient characteristics and major efficacy results are shown in Table 10.

Table 10: Combination Dosage Schedule: Study Results

 | Study 1 |  |  | Study 2
 | Irinotecan + Bolus 5-FU/LV weekly x 4 every 6 weeks | Bolus 5-FU/LV daily x 5 every 4 weeks | Irinotecan weekly x 4 every 6 weeks | Irinotecan + Infusional 5-FU/LV | Infusional 5-FU/LV
Number of patients | 231 | 226 | 226 | 198 | 187
Demographics and treatment administration
Female/Male (%) | 34/65 | 45/54 | 35/64 | 33/67 | 47/53
Median age in years (range) | 62 (25 to 85) | 61 (19 to 85) | 61 (30 to 87) | 62 (27 to 75) | 59 (24 to 75)
Performance status (%) 0 1 2 | 39 46 15 | 41 45 13 | 46 46 8 | 51 42 7 | 51 41 8
Primary tumor (%) Colon Rectum | 81 17 | 85 14 | 84 15 | 55 45 | 65 35
Median time from diagnosis to randomization (months, range) | 1.9 (0 to 161) | 1.7 (0 to 203) | 1.8 (0.1 to 185) | 4.5 (0 to 88) | 2.7 (0 to 104)
Prior adjuvant 5-FU therapy (%) No Yes | 89 11 | 92 8 | 90 10 | 74 26 | 76 24
Median duration of study treatmenta(months) | 5.5 | 4.1 | 3.9 | 5.6 | 4.5
Median Relative Dose Intensity (%)a Irinotecan 5-FU | 72 71 | — 86 | 75 — | 87 86 | — 93
Efficacy Results
Confirmed objective tumor response rateb(%) | 39 | 21 | 18 | 35 | 22
Confirmed objective tumor response rateb(%) | (p<0.0001)c |  |  | (p<0.005)c
Median time to tumor progressiond(months) | 7.0 | 4.3 | 4.2 | 6.7 | 4.4
Median time to tumor progressiond(months) | (p=0.004)d |  |  | (p<0.001)d
Median survival (months) | 14.8 | 12.6 | 12.0 | 17.4 | 14.1
Median survival (months) | (p<0.05)d |  |  | (p<0.05)d

aStudy 1: N=225 (irinotecan/5-FU/LV),N=219 (5-FU/LV),N=223 (irinotecan)

Study 2: N=199 (irinotecan/5-FU/LV),N=186 (5-FU/LV)

bConfirmed ≥ 4 to 6 weeks after first evidence of objective response

cChi-square test

dLog-rank test

Improvement was noted with irinotecan-based combination therapy relative to 5-FU/LV when response rates and time to tumor progression were examined across the following demographic and disease-related subgroups (age, gender, ethnic origin, performance status, extent of organ involvement with cancer, time from diagnosis of cancer, prior adjuvant therapy, and baseline laboratory abnormalities). Figures 1 and 2 illustrate the Kaplan-Meier survival curves for the comparison of irinotecan/5-FU/LV versus 5-FU/LV in Studies 1 and 2, respectively.

Figure 1: Survival First-Line Irinotecan/5-FU/LV vs 5-FU/LV Study 1

Figure 2: Survival First-Line Irinotecan/5-FU/LV vs 5-FU/LV Study 2

Second-Line Therapy After 5-FU-Based Treatment
4 Weekly Doses on a 6-Week Cycle: Studies 3, 4, and 5
Data from three open-label, single-agent, clinical studies, involving a total of 304 patients in 59 centers, support the use of irinotecan hydrochloride injection in the treatment of patients with metastatic cancer of the colon or rectum that has recurred or progressed following treatment with 5-FU-based therapy. These studies were designed to evaluate tumor response rate and do not provide information on effects on survival and disease-related symptoms. In each study, irinotecan hydrochloride injection was administered in repeated 6-week cycles consisting of a 90-minute intravenous infusion once weekly for 4 weeks, followed by a 2-week rest period. Starting doses of irinotecan hydrochloride injection in these trials were 100, 125, or 150 mg/m^2, but the 150-mg/m^2dose was poorly tolerated (due to high rates of grade 4 late diarrhea and febrile neutropenia). Study 3 enrolled 48 patients and was conducted by a single investigator at several regional hospitals. Study 4 was a multicenter study conducted by the North Central Cancer Treatment Group. All 90 patients enrolled in Study 4 received a starting dose of 125 mg/m^2. Study 5 was a multicenter study that enrolled 166 patients from 30 institutions. The initial dose in Study 5 was 125 mg/m^2but was reduced to 100 mg/m^2because the toxicity seen at the 125-mg/m^2dose was perceived to be greater than that seen in previous studies. All patients in these studies had metastatic colorectal cancer, and the majority had disease that recurred or progressed following a 5-FU-based regimen administered for metastatic disease. The results of the individual studies are shown in Table 11.
Table 11: Weekly Dosage Schedule: Study Results

 | Study
 | 3 | 4 | 5
Number of Patients | 48 | 90 | 64 | 102
Starting Dose (mg/m^2/week x 4) | 125a | 125 | 125 | 100
Demographics and Treatment Administration
Female/Male (%) | 46/54 | 36/64 | 50/50 | 51/49
Median Age in years (range) | 63 (29 to 78) | 63 (32 to 81) | 61 (42 to 84) | 64 (25 to 84)
Ethnic Origin (%) White African American Hispanic Oriental/Asian | 79 12 8 0 | 96 4 0 0 | 81 11 8 0 | 91 5 2 2
Performance Status (%) 0 1 2 | 60 38 2 | 38 48 14 | 59 33 8 | 44 51 5
Primary Tumor (%) Colon Rectum Unknown | 100 0 0 | 71 29 0 | 89 11 0 | 87 8 5
Prior 5-FU Therapy (%) For Metastatic Disease ≤ 6 months after Adjuvant > 6 months after Adjuvant Classification Unknown | 81 15 2 2 | 66 7 16 12 | 73 27 0 0 | 68 28 2 3
Prior Pelvic/Abdominal Irradiation (%) Yes Other None | 3 0 97 | 29 9 62 | 0 2 98 | 0 4 96
Duration of Treatment with irinotecan (median, months) | 5 | 4 | 4 | 3
Relative Dose Intensityb(median %) | 74 | 67 | 73 | 81
Efficacy
Confirmed Objective Response Rate (%)c (95% CI) | 21 (9.3 to 32.3) | 13 (6.3 to 20.4) | 14 (5.5 to 22.6) | 9 (3.3 to 14.3)
Time to Response (median, months) | 2.6 | 1.5 | 2.8 | 2.8
Response Duration (median, months) | 6.4 | 5.9 | 5.6 | 6.4
Survival (median, months) | 10.4 | 8.1 | 10.7 | 9.3
1-Year Survival (%) | 46 | 31 | 45 | 43

aNine patients received 150 mg/m^2as a starting dose; two (22.2%) responded to irinotecan hydrochloride injection.
bRelative dose intensity for irinotecan hydrochloride injection based on planned dose intensity of 100, 83.3, and 66.7 mg/m^2/wk corresponding with 150, 125, and 100 mg/m^2starting doses, respectively.
cConfirmed ≥ 4 to 6 weeks after first evidence of objective response.

In the intent-to-treat analysis of the pooled data across all three studies, 193 of the 304 patients began therapy at the recommended starting dose of 125 mg/m^2. Among these 193 patients, 2 complete and 27 partial responses were observed, for an overall response rate of 15.0% (95% Confidence Interval [CI], 10.0% to 20.1%) at this starting dose. A considerably lower response rate was seen with a starting dose of 100 mg/m^2. The majority of responses were observed within the first two cycles of therapy, but responses did occur in later cycles of treatment (one response was observed after the eighth cycle). The median response duration for patients beginning therapy at 125 mg/m^2was 5.8 months (range, 2.6 to 15.1 months). Of the 304 patients treated in the three studies, response rates to irinotecan hydrochloride injection were similar in males and females and among patients older and younger than 65 years. Rates were also similar in patients with cancer of the colon or cancer of the rectum and in patients with single and multiple metastatic sites. The response rate was 18.5% in patients with a performance status of 0 and 8.2% in patients with a performance status of 1 or 2. Patients with a performance status of 3 or 4 have not been studied. Over half of the patients responding to irinotecan hydrochloride injection had not responded to prior 5-FU. Patients who had received previous irradiation to the pelvis responded to irinotecan hydrochloride injection at approximately the same rate as those who had not previously received irradiation.

Once-Every-3-Week Dosage Schedule

Single Arm Study: Study 6

Data from an open-label, single-agent, single-arm, multicenter, clinical study involving a total of 132 patients support a once every-3-week dosage schedule of irinotecan in the treatment of patients with metastatic cancer of the colon or rectum that recurred or progressed following treatment with 5-FU. Patients received a starting dose of 350 mg/m^2given by 30-minute intravenous infusion once every 3 weeks. Among the 132 previously treated patients in this trial, the intent-to-treat response rate was 12.1% (95% CI, 7.0% to 18.1%).

Randomized Studies: Studies 7 and 8

Two multicenter, randomized, clinical studies further support the use of irinotecan given by the once-every-3-week dosage schedule in patients with metastatic colorectal cancer whose disease has recurred or progressed following prior 5-FU therapy. In Study 7, second-line irinotecan therapy plus best supportive care was compared with best supportive care alone. In Study 8, second-line irinotecan therapy was compared with infusional 5-FU-based therapy. In both studies, irinotecan was administered intravenously at a starting dose of 350 mg/m^2over 90 minutes once every 3 weeks. The starting dose was 300 mg/m^2for patients who were 70 years and older or who had a performance status of 2. The highest total dose permitted was 700 mg. Dose reductions and/or administration delays were permitted in the event of severe hematologic and/or nonhematologic toxicities while on treatment. Best supportive care was provided to patients in both arms of Study 7 and included antibiotics, analgesics, corticosteroids, transfusions, psychotherapy, or any other symptomatic therapy as clinically indicated. In both studies, concomitant medications such as antiemetics, atropine, and loperamide were given to patients for prophylaxis and/or management of symptoms from treatment. If late diarrhea persisted for greater than 24 hours despite loperamide, a 7-day course of fluoroquinolone antibiotic prophylaxis was given. Patients in the control arm of the Study 8 received one of the following 5-FU regimens: (1) LV, 200 mg/m^2IV over 2 hours; followed by 5-FU, 400 mg/m^2IV bolus; followed by 5-FU, 600 mg/m^2continuous IV infusion over 22 hours on days 1 and 2 every 2 weeks; (2) 5-FU, 250 to 300 mg/m^2/day protracted continuous IV infusion until toxicity; (3) 5-FU, 2.6 to 3 g/m^2IV over 24 hours every week for 6 weeks with or without LV, 20 to 500 mg/m^2/day every week IV for 6 weeks with 2-week rest between cycles. Patients were to be followed every 3 to 6 weeks for 1 year.

A total of 535 patients were randomized in the two studies at 94 centers. The primary endpoint in both studies was survival. The studies demonstrated a significant overall survival advantage for irinotecan compared with best supportive care (p=0.0001) and infusional 5-FU-based therapy (p=0.035) as shown in Figures 3 and 4. In Study 7, median survival for patients treated with irinotecan was 9.2 months compared with 6.5 months for patients receiving best supportive care. In Study 8, median survival for patients treated with irinotecan was 10.8 months compared with 8.5 months for patients receiving infusional 5-FU-based therapy. Multiple regression analyses determined that patients' baseline characteristics also had a significant effect on survival. When adjusted for performance status and other baseline prognostic factors, survival among patients treated with irinotecan remained significantly longer than in the control populations (p=0.001 for Study 7 and p=0.017 for Study 8). Measurements of pain, performance status, and weight loss were collected prospectively in the two studies; however, the plan for the analysis of these data was defined retrospectively. When comparing irinotecan with best supportive care in Study 7, this analysis showed a statistically significant advantage for irinotecan, with longer time to development of pain (6.9 months versus 2.0 months), time to performance status deterioration (5.7 months versus 3.3 months), and time to > 5% weight loss (6.4 months versus 4.2 months). Additionally, 33.3% (33/99) of patients with a baseline performance status of 1 or 2 showed an improvement in performance status when treated with irinotecan versus 11.3% (7/62) of patients receiving best supportive care (p=0.002). Because of the inclusion of patients with non-measurable disease, intent-to-treat response rates could not be assessed.

Figure 3: Survival Second-Line Irinotecan vs Best Supportive Care (BSC) Study 7

Figure 4: Survival Second-Line Irinotecan vs Infusion 5-FU Study 8

Table 12: Once-Every-3-Week Dosage Schedule: Study Results

 | Study 7 |  | Study 8
 | Irinotecan | BSCa | Irinotecan | 5-FU
Number of patients | 189 | 90 | 127 | 129
Demographics and treatment administration
Female/Male (%) | 32/68 | 42/58 | 43/57 | 35/65
Median age in years (range) | 59 (22 to 75) | 62 (34 to 75) | 58 (30 to 75) | 58 (25 to 75)
Performance status (%) 0 1 2 | 47 39 14 | 31 46 23 | 58 35 8 | 54 43 3
Primary tumor (%) Colon Rectum | 55 45 | 52 48 | 57 43 | 62 38
Prior 5-FU therapy (%) For metastatic disease As adjuvant treatment | 70 30 | 63 37 | 58 42 | 68 32
Prior irradiation (%) | 26 | 27 | 18 | 20
Duration of study treatment (median, months)(Log-rank test) | 4.1 | --‑ | 4.2 (p=0.02) | 2.8
Relative dose intensity (median %)b | 94 | --‑ | 95 | 81 to 99
Survival
Survival (median, months) (Log-rank test) | 9.2 (p=0.0001) | 6.5 | 10.8 (p=0.035) | 8.5

aBSC = best supportive care
bRelative dose intensity for irinotecan based on planned dose intensity of 116.7 and 100 mg/m^2/wk corresponding with 350 and 300 mg/m^2starting doses, respectively.

In the two randomized studies, the EORTC QLQ-C30 instrument was utilized. At the start of each cycle of therapy, patients completed a questionnaire consisting of 30 questions, such as "Did pain interfere with daily activities?" (1 = Not at All, to 4 = Very Much) and "Do you have any trouble taking a long walk?" (Yes or No). The answers from the 30 questions were converted into 15 subscales, that were scored from 0 to 100, and the global health status subscale that was derived from two questions about the patient’s sense of general well being in the past week. The results as summarized in Table 13 are based on patients’ worst post-baseline scores. In Study 7, a multivariate analysis and univariate analyses of the individual subscales were performed and corrected for multivariate testing. Patients receiving irinotecan reported significantly better results for the global health status, on two of five functional subscales, and on four of nine symptom subscales. As expected, patients receiving irinotecan noted significantly more diarrhea than those receiving best supportive care. In Study 8, the multivariate analysis on all 15 subscales did not indicate a statistically significant difference between irinotecan and infusional 5-FU.

Table 13: EORTC QLQ-C30: Mean Worst Post-Baseline Scorea

QLQ-C30 Subscale | Study 7 |  |  | Study 8
 | Irinotecan | BSC | p-value | Irinotecan | 5-FU | p-value
Global health status | 47 | 37 | 0.03 | 53 | 52 | 0.9
Functional scales
Cognitive | 77 | 68 | 0.07 | 79 | 83 | 0.9
Emotional | 68 | 64 | 0.4 | 64 | 68 | 0.9
Social | 58 | 47 | 0.06 | 65 | 67 | 0.9
Physical | 60 | 40 | 0.0003 | 66 | 66 | 0.9
Role | 53 | 35 | 0.02 | 54 | 57 | 0.9
Symptom Scales
Fatigue | 51 | 63 | 0.03 | 47 | 46 | 0.9
Appetite loss | 37 | 57 | 0.0007 | 35 | 38 | 0.9
Pain assessment | 41 | 56 | 0.009 | 38 | 34 | 0.9
Insomnia | 39 | 47 | 0.3 | 39 | 33 | 0.9
Constipation | 28 | 41 | 0.03 | 25 | 19 | 0.9
Dyspnea | 31 | 40 | 0.2 | 25 | 24 | 0.9
Nausea/Vomiting | 27 | 29 | 0.5 | 25 | 16 | 0.09
Financial impact | 22 | 26 | 0.5 | 24 | 15 | 0.3
Diarrhea | 32 | 19 | 0.01 | 32 | 22 | 0.2

aFor the five functional subscales and global health status subscale, higher scores imply better functioning, whereas, on the nine symptom subscales, higher scores imply more severe symptoms. The subscale scores of each patient were collected at each visit until the patient dropped out of the study.

15 REFERENCES

1. “OSHA Hazardous Drugs.” OSHA. http://www.osha.gov/SLTC/hazardousdrugs/index.html

16 HOW SUPPLIED/STORAGE AND HANDLING

Irinotecan hydrochloride injection, USP is supplied as a sterile, pale yellow, clear, aqueous solution and is available in single-dose brown glass vials in the following package sizes:

PRESENTATION | NDC CODE
2 mL-fill vial containing 40 mg/2 mL (20 mg/mL) irinotecan hydrochloride injection | NDC 70700-169-22
5 mL- fill vial containing 100 mg/5 mL(20 mg/mL) irinotecan hydrochloride injection | NDC 70700-170-22

Store at 20° to25°C (68° to 77°F) [see USP Controlled Room Temperature].Protect from light.

Keep the vial in the carton until the time of use.

Inspect the vial for damage and visible signs of leaks before removing from the carton. If damaged, incinerate the unopened package.

Irinotecan hydrochloride is a hazardous drug. Follow special handling and disposal procedures.^1

17 PATIENT COUNSELING INFORMATION

• Patients and caregivers should be informed of gastrointestinal complications, such as nausea, vomiting, abdominal cramping, and diarrhea. Patients should have loperamide readily available to begin treatment for late diarrhea (generally occurring more than 24 hours after administration of irinotecan hydrochloride injection). Begin loperamide at the first episode of poorly formed or loose stools or the earliest onset of bowel movements more frequent than normal. One dosage regimen for loperamide is 4 mg at the first onset of late diarrhea and then 2 mg every 2 hours until the patient is diarrhea-free for at least 12 hours. Loperamide is not recommended to be used for more than 48 consecutive hours at these doses, because of the risk of paralytic ileus. During the night, the patient may take 4 mg of loperamide every 4 hours. Patients should contact their physician if any of the following occur: diarrhea for the first time during treatment; black or bloody stools; symptoms of dehydration such as lightheadedness, dizziness, or faintness; inability to take fluids by mouth due to nausea or vomiting; or inability to get diarrhea under control within 24 hours.
• Patients should be warned about the potential for dizziness or visual disturbances which may occur within 24 hours following the administration of irinotecan hydrochloride injection.
• Explain the significance of routine blood cell counts. Instruct patients to monitor their temperature frequently and immediately report any occurrence of fever or infection.
• Embryo-Fetal Toxicity [see Warnings and Precautions (5.9), Use in Specific Populations (8.18.3), Clinical Pharmacology (12.1)and Nonclinical Toxicology (13.1)]
o Advise pregnant women and females of reproductive potential of the potential risk to a fetus and to inform their healthcare provider of a known or suspected pregnancy.
o Advise females of reproductive potential to use effective contraception during treatment with irinotecan hydrochloride injection and for 6 months after the final dose.
o Advise male patients with female partners of reproductive potential to use condoms during treatment and for 3 months after the final dose of irinotecan hydrochloride injection.
• Lactation
o Advise women not to breastfeed during treatment with irinotecan hydrochloride injection and for at least 7 days after the final dose [see Use in Specific Populations (8.2)].
• Infertility
o Advise females and males of reproductive potential that irinotecan hydrochloride injection may impair fertility [see Use in Specific Populations (8.3)].
• Patients should be alerted to the possibility of alopecia.
• Contains sorbitol.

Manufactured For:
Xiromed, LLC.
Florham Park, NJ 07932

Product of India

Revised: 02/2022
PI-169-03

PSLEA-020347-02

PACKAGE LABEL.PRINCIPAL DISPLAY PANEL - 20 mg/mL - 2 mL VIAL LABEL

NDC 70700-169-22 Rx Only
Irinotecan Hydrochloride Injection, USP
40 mg/2 mL
(20 mg/mL)
For Intravenous Use only
Must be diluted before use
Caution: Cytotoxic Agent
2 mL Single Dose Vial

PACKAGE LABEL.PRINCIPAL DISPLAY PANEL - 20 mg/mL - 2 mL CARTON LABEL
NDC 70700-169-22 Rx Only
Irinotecan Hydrochloride Injection, USP
40 mg/2 mL
(20 mg/mL)
For Intravenous Use only
Must be diluted before use

Caution: Cytotoxic Agent
2 mL Single Dose Vial
Discard unused portion

PACKAGE LABEL.PRINCIPAL DISPLAY PANEL - 20 mg/mL - 5 mL VIAL LABEL
NDC 70700-170-22 Rx Only
Irinotecan Hydrochloride Injection, USP
100 mg/5 mL
(20 mg/mL)
For Intravenous Use only
Must be diluted before use
Caution: Cytotoxic Agent
5 mL Single Dose Vial

PACKAGE LABEL.PRINCIPAL DISPLAY PANEL - 20 mg/mL - 5 mL CARTON LABEL
NDC 70700-170-22 Rx Only
Irinotecan Hydrochloride Injection, USP
100 mg/5 mL
(20 mg/mL)
For Intravenous Use only
Must be diluted before use
Caution: Cytotoxic Agent
5 mL Single Dose Vial
Discard unused portion